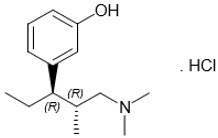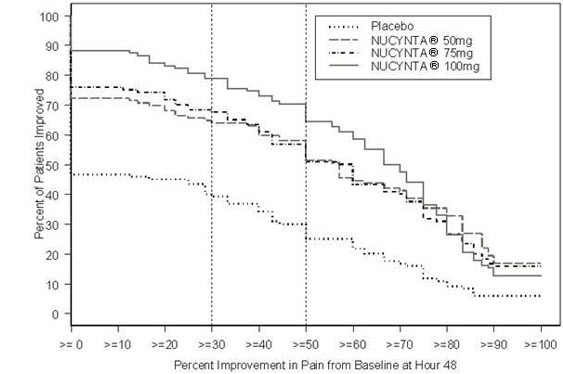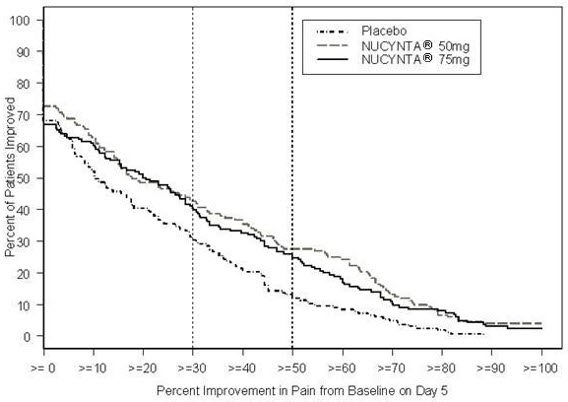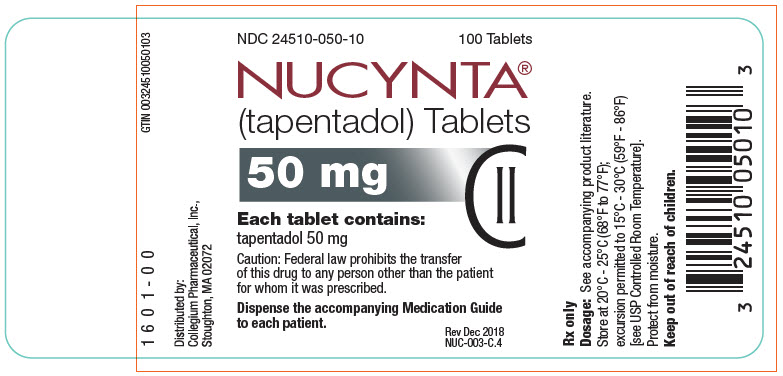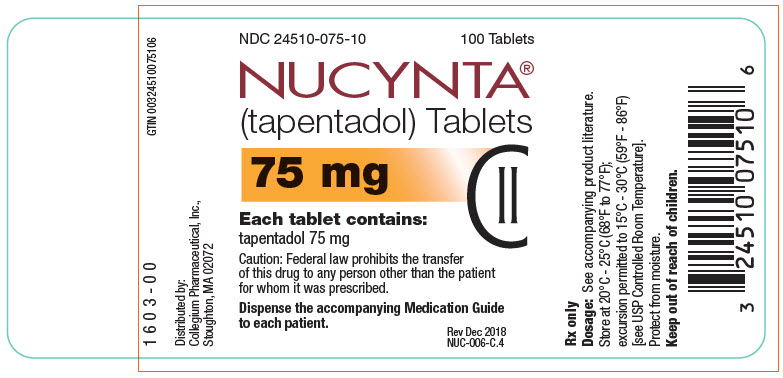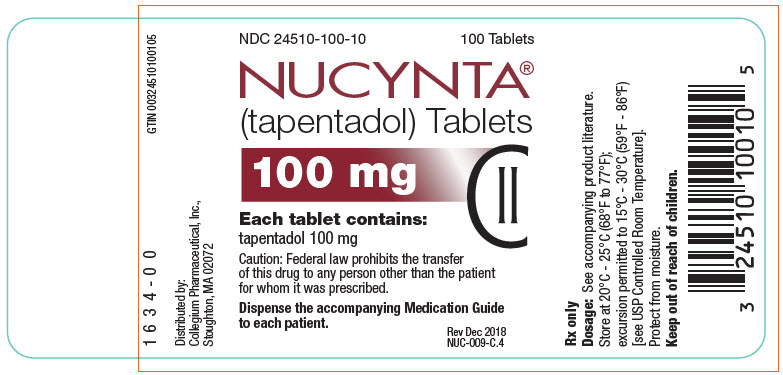 DRUG LABEL: Nucynta
NDC: 24510-050 | Form: TABLET, FILM COATED
Manufacturer: Collegium Pharmaceutical, Inc.
Category: prescription | Type: HUMAN PRESCRIPTION DRUG LABEL
Date: 20251230
DEA Schedule: CII

ACTIVE INGREDIENTS: TAPENTADOL HYDROCHLORIDE 50 mg/1 1
INACTIVE INGREDIENTS: MICROCRYSTALLINE CELLULOSE; LACTOSE MONOHYDRATE; CROSCARMELLOSE SODIUM; POVIDONE, UNSPECIFIED; MAGNESIUM STEARATE; POLYVINYL ALCOHOL, UNSPECIFIED; TITANIUM DIOXIDE; POLYETHYLENE GLYCOL, UNSPECIFIED; TALC; ALUMINUM OXIDE

HIGHLIGHTS OF PRESCRIBING INFORMATION

These highlights do not include all the information needed to use NUCYNTA® TABLETS safely and effectively. See full prescribing information for NUCYNTA® TABLETS.
NUCYNTA® (tapentadol) tablets for oral use C-II
Initial U.S. Approval: 2008

WARNING: SERIOUS AND LIFE-THREATENING RISKS FROM USE OF NUCYNTA TABLETS

See full prescribing information for complete boxed warning.

- NUCYNTA tablets expose users to risks of addiction, abuse, and misuse, which can lead to overdose and death. Assess patient's risk before prescribing and reassess regularly for these behaviors and conditions. (5.1)
- Serious, life-threatening, or fatal respiratory depression may occur, especially upon initiation or following a dosage increase. To reduce the risk of respiratory depression, proper dosing and titration of NUCYNTA tablets are essential. (5.2)
- Concomitant use of opioids with benzodiazepines or other central nervous system (CNS) depressants, including alcohol, may result in profound sedation, respiratory depression, coma, and death. Reserve concomitant prescribing for use in patients for whom alternative treatment options are inadequate. (5.3, 7)
- Accidental ingestion of NUCYNTA tablets, especially by children, can result in a fatal overdose of tapentadol. (5.2)
- Advise pregnant women using opioids for an extended period of time of the risk of Neonatal Opioid Withdrawal Syndrome, which may be life-threatening if not recognized and treated. Ensure that management by neonatology experts will be available at delivery. (5.4)
- Healthcare providers are strongly encouraged to complete a REMS-compliant education program and to counsel patients and caregivers on serious risks, safe use, and the importance of reading the Medication Guide with each prescription. (5.5)

RECENT MAJOR CHANGES

Boxed Warning | 12/2025
Indications and Usage (1) | 12/2025
Dosage and Administration (2.2, 2.7) | 12/2025
Warnings and Precautions (5.1, 5.2, 5.3, 5.12, 5.14) | 12/2025

1 INDICATIONS AND USAGE

NUCYNTA tablets are an opioid analgesic indicated for the management of acute pain severe enough to require an opioid analgesic and for which alternative treatments are inadequate in adults and pediatric patients aged 6 years and older with a body weight of at least 40 kg. (1)

Limitations of Use
Because of the risks of addiction, abuse, misuse, overdose, and death, which can occur at any dosage or duration, and persist over the course of therapy, reserve opioid analgesics, including NUCYNTA tablets for use in patients for whom alternative treatment options are

ineffective, not tolerated, or would be otherwise inadequate to provide sufficient management of pain. (1, 5.1)

2 DOSAGE AND ADMINISTRATION

- NUCYNTA tablets should be prescribed only by healthcare professionals who are knowledgeable about the use of opioids and how to mitigate the associated risks. (2.1)
- Use the lowest effective dosage for the shortest duration consistent with individual patient treatment goals. Reserve titration to higher doses of NUCYNTA tablets for patients in whom lower doses are insufficiently effective and in whom the expected benefits of using a higher dose opioid clearly outweigh the substantial risks. (2.1, 5)
- Many acute pain conditions (e.g., the pain that occurs with a number of surgical procedures or acute musculoskeletal injuries) require no more than a few days of an opioid analgesic. Clinical guidelines on opioid prescribing for some acute pain conditions are available. (2.1)
- Initiate the dosing regimen for each patient individually, taking into account the patient's underlying cause and severity of pain, prior analgesic treatment and response, and risk factors for addiction, abuse, and misuse. (2.1, 5.1)
- Respiratory depression can occur at any time during opioid therapy, especially when initiating and following dosage increases with NUCYNTA tablets. Consider this risk when selecting an initial dose and when making dose adjustments. (2.1, 5.2)
- NUCYNTA tablets can be taken with or without food (2.1).
- Discuss opioid overdose reversal agents and options for acquiring them with the patient and/or caregiver, both when initiating andrenewing treatment with NUCYNTA tablets, especially if the patient has additional risk factors for overdose, or close contacts at risk for exposure and overdose. (2.2, 5.1, 5.2, 5.3)
- Dosing in adults: See full prescribing information for detailed dosing instructions. (2.3)
- Dosing in Pediatric Patients aged 6 years and older with a body weight of at least 40 kg and who are able to swallow tablets: See full prescribing information for detailed dosing instructions. (2.4)
- Moderate Hepatic Impairment in Adult Patients: Initiate treatment with 50 mg no more than once every 8 hours (maximum of three doses in 24 hours). Regularly evaluate for respiratory and central nervous system depression. (2.4)
- Periodically reassess patients receiving NUCYNTA tablets to evaluate the continued need for opioid analgesics to maintain pain control, for the signs or symptoms of adverse reactions, and for the development of addiction, abuse, or misuse. (2.6)
- Do not rapidly reduce or abruptly discontinue NUCYNTA tablets in a physically dependent patient because rapid reduction or abrupt discontinuation of opioid analgesics has resulted in serious withdrawal symptoms, uncontrolled pain, and suicide. (2.6, 5.14)

3 DOSAGE FORMS AND STRENGTHS

Tablets: 50 mg, 75 mg, 100 mg (3)

4 CONTRAINDICATIONS

- Significant respiratory depression (4)
- Acute or severe bronchial asthma in an unmonitored setting or in absence of resuscitative equipment. (4)
- Known or suspected gastrointestinal obstruction, including paralytic ileus (4)
- Hypersensitivity to tapentadol (4)
- Concurrent use of monoamine oxidase inhibitors (MAOIs) or use of MAOIs within the last 14 days. (4)

5 WARNINGS AND PRECAUTIONS

- Opioid-Induced Hyperalgesia and Allodynia: Opioid-Induced Hyperalgesia (OIH) occurs when an opioid analgesic paradoxically causes an increase in pain, or an increase in sensitivity to pain. If OIH is suspected, carefully consider appropriately decreasing the dose of the current opioid analgesic, or opioid rotation. (5.6)
- Serotonin Syndrome with Concomitant Use of Serotonergic Drugs: Potentially life-threatening condition could result from concomitant serotonergic drug administration. Discontinue NUCYNTA tablets if serotonin syndrome is suspected. (5.7)
- Life-Threatening Respiratory Depression in Patients with Chronic Pulmonary Disease or in Elderly, Cachectic, or Debilitated Patients: Regularly evaluate, particularly during initiation and titration. (5.8)
- Adrenal Insufficiency: If diagnosed, treat with physiologic replacement of corticosteroids, and wean patient off of the opioid. (5.8)
- Severe Hypotension: Regularly evaluate during dosage initiation and titration. Avoid use of NUCYNTA tablets in patients with circulatory shock. (5.10)
- Risks of Use in Patients with Increased Intracranial Pressure, Brain Tumors, Head Injury, or Impaired Consciousness: Monitor for sedation and respiratory depression. Avoid use of NUCYNTA tablets in patients with impaired consciousness or coma. (5.11)

6 ADVERSE REACTIONS

The most common adverse reactions were

- Adults (incidence ≥10%) were nausea, dizziness, vomiting and somnolence. (6.1)
- Pediatric patients 6 years and older (incidence ≥5%): vomiting, constipation, nausea, pruritus, and pyrexia

To report SUSPECTED ADVERSE REACTIONS, contact Collegium Pharmaceutical, Inc. at 1-855-331-5615 or FDA at 1-800-FDA-1088 or www.fda.gov/medwatch

7 DRUG INTERACTIONS

- Mixed Agonist/Antagonist and Partial Agonist Opioid Analgesics: Avoid use with NUCYNTA tablets because they reduce analgesic effect of NUCYNTA tablets or precipitate withdrawal symptoms. (7).

8 USE IN SPECIFIC POPULATIONS

- Pregnancy: May cause fetal harm. (8.1)
- Lactation: Closely monitor infants of nursing women receiving NUCYNTA tablets. (8.2)
- Severe Renal or Hepatic Impairment: Not recommended. (8.6, 8.7)
- Pediatric Patients with Hepatic or Renal Impairment: Use not recommended. (2.4, 8.4)

FULL PRESCRIBING INFORMATION

WARNING: SERIOUS AND LIFE-THREATENING RISKS FROM USE OF NUCYNTA TABLETS

Addiction, Abuse, and Misuse

Because the use of NUCYNTA tablets exposes patients and other users to the risks of opioid addiction, abuse, and misuse, which can lead to overdose and death, assess each patient's risk prior to prescribing and reassess all patients regularly for the development of these behaviors and conditions [see Warnings and Precautions (5.1)].

Life-Threatening Respiratory Depression

Serious, life-threatening, or fatal respiratory depression may occur with use of NUCYNTA tablets, especially during initiation or following a dosage increase. To reduce the risk of respiratory depression, proper dosing and titration of NUCYNTA tablets are essential [see Warnings and Precautions (5.2)].

Accidental Ingestion

Accidental ingestion of even one dose of NUCYNTA tablets, especially by children, can result in a fatal overdose of tapentadol [see Warnings and Precautions (5.2)].

Risks From Concomitant Use With Benzodiazepines Or Other CNS Depressants

Concomitant use of opioids with benzodiazepines or other central nervous system (CNS) depressants, including alcohol, may result in profound sedation, respiratory depression, coma, and death. Reserve concomitant prescribing of NUCYNTA tablets and benzodiazepines or other CNS depressants for use in patients for whom alternative treatment options are inadequate [see Warnings and Precautions (5.3), Drug Interactions (7)].

Neonatal Opioid Withdrawal Syndrome (NOWS)

Advise pregnant women using opioids for an extended period of time of the risk of Neonatal Opioid Withdrawal Syndrome, which may be life-threatening if not recognized and treated. Ensure that management by neonatology experts will be available at delivery [see Warnings and Precautions (5.4)].

Opioid Analgesic Risk Evaluation and Mitigation Strategy (REMS)

Healthcare providers are strongly encouraged to complete a REMS-compliant education program and to counsel patients and caregivers on serious risks, safe use, and the importance of reading the Medication Guide with each prescription [see Warnings and Precautions (5.5)].

1 INDICATIONS AND USAGE

NUCYNTA (tapentadol) tablets are indicated for the management of acute pain severe enough to require an opioid analgesic and for which alternative treatments are inadequate in adults and pediatric patients aged 6 years and older with a body weight of at least 40kg.

Limitations of Use

Because of the risks of addiction, abuse, misuse, overdose, and death, which can occur at any dose or duration [see Warnings and Precautions (5.1)], and persist over the course of therapy, reserve opioid analgesics, including NUCYNTA tablets for use in patients for whom alternative treatment options are ineffective, not tolerated, or would be otherwise inadequate to provide sufficient management of pain.

2 DOSAGE AND ADMINISTRATION

2.1 IMPORTANT DOSAGE AND ADMINISTRATION INSTRUCTIONS

- NUCYNTA tablets should be prescribed only by healthcare professionals who are knowledgeable about the use of opioids and how to mitigate the associated risks.
- Use the lowest effective dosage for the shortest duration of time consistent with individual patient treatment goals [see Warnings and Precautions (5)]. Because the risk of overdose increases as opioid doses increase, reserve titration to higher doses of NUCYNTA tablets for patients in whom lower doses are insufficiently effective and in whom the expected benefits of using a higher dose opioid clearly outweigh the substantial risks.
- Many acute pain conditions (e.g., the pain that occurs with a number of surgical procedures or acute musculoskeletal injuries) require no more than a few days of an opioid analgesic. Clinical guidelines on opioid prescribing for some acute pain conditions are available.
- There is variability in the opioid analgesic dose and duration needed to adequately manage pain due both to the cause of pain and to individual patient factors. Initiate the dosing regimen for each patient individually, taking into account the patient's underlying cause and severity of pain, prior analgesic treatment and response, and risk factors for addiction, abuse, and misuse [see Warnings and Precautions (5.1)].
- Respiratory depression can occur at any time during opioid therapy, especially when initiating and following dosage increases with NUCYNTA tablets. Consider this risk when selecting an initial dose and when making dose adjustments [see Warnings and Precautions (5)].
- NUCYNTA tablets can be taken with or without food [see Clinical Pharmacology (12.3)].

2.2 PATIENT ACCESS TO AN OPIOID OVERDOSE REVERSAL AGENTAGENT FOR THE EMERGENCY TREATMENT OF OPIOID OVERDOSE

Inform patients and caregivers about opioid overdose reversal agents (e.g., naloxone, nalmefene). Discuss the importance of having access to an opioid overdose reversal agent, especially if the patient has risk factors for overdose (e.g., concomitant use of CNS depressants, a history of opioid use disorder, or prior opioid overdose) or if there are household members (including children) or other close contacts at risk for accidental ingestion or opioid overdose. The presence of risk factors for overdose should not prevent the management of pain in any patient [see Warnings and Precautions (5.1, 5.2, 5.3)].

Discuss the options for obtaining an opioid overdose reversal agent (e.g., prescription, over-the-counter, or as part of a community-based program) [see Warnings and Precautions (5.3)].

There are important differences among the opioid overdose reversal agents, such as route of administration, product strength, approved patient age range, and pharmacokinetics. Be familiar with these differences, as outlined in the approved labeling for those products, prior to recommending or prescribing such an agent.

2.3 INITIAL DOSAGE IN ADULTS

Initiating Treatment with NUCYNTA Tablets

Initiate treatment with NUCYNTA tablets in a dosing range of 50 mg to 100 mg every 4 to 6 hours as needed for pain, and at the lowest dose necessary to achieve adequate analgesia. Titrate the dose based upon the individual patient's response to their initial dose of NUCYNTA tablets.

On the first day of dosing, the second dose may be administered as soon as one hour after the first dose, if adequate pain relief is not attained with the first dose. Subsequent dosing is 50 mg, 75 mg, or 100 mg every 4 to 6 hours and should be adjusted to maintain adequate analgesia with acceptable tolerability.

Daily doses greater than 700 mg on the first day of therapy and 600 mg on subsequent days have not been studied and are not recommended.

NUCYNTA tablets may be given with or without food [see Clinical Pharmacology (12.3)].

Conversion from NUCYNTA Tablets to NUCYNTA ER

Patients can be converted from NUCYNTA tablets to NUCYNTA ER using the equivalent total daily dose of NUCYNTA tablets and dividing it into two equal doses of NUCYNTA ER separated by approximately 12-hour intervals. As an example, a patient receiving 50 mg of NUCYNTA tablets four times per day (200 mg/day) may be converted to 100 mg NUCYNTA ER twice a day. Conversion to NUCYNTA ER may lead to increased risk of excessive sedation and respiratory depression.

2.4 DOSAGE IN PEDIATRIC PATIENTS 6 YEARS AND OLDER WITH BODY WEIGHT OF AT LEAST 40 KG

Pediatric patients who are at least 6 years old, weigh at least 40 kg, and are able to swallow oral tablets:

For patients weighing 40 to 59 kg, administer 50 mg every 4 hours. Do not exceed a maximum single dose of 50 mg. If adequate analgesia is not achieved with a 50 mg NUCYNTA tablet every 4 hours, do not increase to a 75 mg NUCYNTA tablet. Instead consider use of another NUCYNTA product that allows for more flexible dosing, such as NUCYNTA oral solution.

For patients weighing 60 to 79 kg, initiate treatment with 50 mg every 4 hours. Increase the dose if needed to 75 mg every 4 hours to maintain adequate analgesia with acceptable tolerability. Do not exceed a maximum single dose of 75 mg. If adequate analgesia is not achieved with a 75 mg NUCYNTA tablet every 4 hours, do not increase to a 100 mg NUCYNTA tablet. Instead consider use of another NUCYNTA product that allows for more flexible dosing, such as NUCYNTA oral solution.

For patients weighing greater than or equal to 80 kg, initiate treatment with 50 mg every 4 hours. Increase the dose if needed to 75 mg every 4 hours to maintain adequate analgesia with acceptable tolerability. If adequate pain relief is not attained with a 75 mg NUCYNTA tablet every 4 hours, increase the dose to 100 mg every 4 hours to maintain adequate analgesia with acceptable tolerability. Do not exceed a maximum single dose of 100 mg.

The maximum daily dose is 7.5 mg/kg/day (i.e., six 1.25 mg/kg doses over 24 hours).

Daily doses greater than 600 mg have not been studied in pediatric patients and are not recommended.

In pediatric patients with high body mass index (BMI), the maximum daily dose must not exceed the calculated maximum dose for a body weight at the 97th percentile for a given age.

The efficacy and safety of NUCYNTA (tapentadol) tablets at doses higher than 1.25 mg/kg body weight (maximum single dose of 100 mg) have not been studied; therefore, the use of NUCYNTA (tapentadol) tablets at doses higher than 1.25 mg/kg body weight is not recommended [see Clinical Studies (14.2)].

Dose reductions may be considered over time as acute pain decreases.

NUCYNTA tablets are not recommended for use in pediatric patients who weigh less than 40 kg as the recommended dose cannot be achieved with available tablet strengths. Consider use of another NUCYNTA product, such as NUCYNTA oral solution, in patients who cannot swallow oral tablets or who weigh less than 40 kg [see Pediatric Use (8.4)].

Duration of Treatment

NUCYNTA (tapentadol) tablets are intended for the management of acute pain severe enough to require an opioid analgesic and for which alternative treatments are inadequate. As with all symptomatic treatments, the continued use of tapentadol must be evaluated on an ongoing basis. In pediatric patients, the duration of treatment should not exceed 3 days as the safety and effectiveness of longer treatment have not been established.

Hepatic or Renal Impairment

NUCYNTA (tapentadol) tablets have not been studied in pediatric patients with hepatic or renal impairment; therefore, use in these populations is not recommended [see Pediatric Use (8.4)].

2.5 DOSAGE MODIFICATIONS IN ADULT PATIENTS WITH HEPATIC IMPAIRMENT

The safety and efficacy of NUCYNTA tablets have not been studied in patients with severe hepatic impairment (Child-Pugh Score 10-15) and use in this population is not recommended [see Warnings and Precautions (5.17)].

Initiate treatment of patients with moderate hepatic impairment (Child-Pugh Score 7 to 9) with 50 mg no more frequently than once every 8 hours (maximum of three doses in 24 hours).

Further treatment should reflect maintenance of analgesia with acceptable tolerability, to be achieved by either shortening or lengthening the dosing interval. Regularly evaluate patients for respiratory and central nervous system depression [see Clinical Pharmacology (12.3)].

No dosage adjustment is recommended in patients with mild hepatic impairment (Child-Pugh Score 5 to 6) [see Clinical Pharmacology (12.3)].

2.6 TITRATION AND MAINTENANCE OF THERAPY

Individually titrate NUCYNTA tablets to a dose that provides adequate analgesia and minimizes adverse reactions. Continually reevaluate patients receiving NUCYNTA tablets to assess the maintenance of pain control, signs and symptoms of opioid withdrawal, and other adverse reactions, as well as reassess for the development of addiction, abuse, or misuse [see Warnings and Precautions (5.1, 5.14)]. Frequent communication is important among the prescriber, other members of the healthcare team, the patient, and the caregiver/family during periods of changing analgesic requirements, including initial titration.

If the level of pain increases after dosage stabilization, attempt to identify the source of increased pain before increasing the NUCYNTA tablets dosage. If after increase the dosage, unacceptable opioid-related adverse reactions are observed (including an increase in pain after a dosage increase), consider reducing the dosage. Adjust the dosage to obtain an appropriate balance between management of pain and opioid-related adverse reactions.

2.7 SAFE REDUCTION OR DISCONTINUATION OF NUCYNTA TABLETS

Do not rapidly reduce or abruptly discontinue NUCYNTA tablets in patients who may be physically dependent on opioids. Rapid reduction or abrupt discontinuation of opioid analgesics in patients who are physically dependent on opioids has resulted in serious withdrawal symptoms, uncontrolled pain, and suicide. Rapid reduction or abrupt discontinuation has also been associated with attempts to find other sources of opioid analgesics, which may be confused with drug-seeking for abuse. Patients may also attempt to treat their pain or withdrawal symptoms with illicit opioids, such as heroin, and other substances.

When a decision has been made to decrease the dose or discontinue therapy in an opioid-dependent patient taking NUCYNTA tablets, there are a variety of factors that should be considered, including the total daily dose of opioid (including NUCYNTA tablets) the patient has been taking, the duration of treatment, the type of pain being treated, and the physical and psychological attributes of the patient. It is important to ensure ongoing care of the patient and to agree on an appropriate tapering schedule and follow-up plan so that patient and provider goals and expectations are clear and realistic. When opioid analgesics are being discontinued due to a suspected substance use disorder, evaluate and treat the patient, or refer for evaluation and treatment of the substance use disorder. Treatment should include evidence-based approaches, such as medication assisted treatment of opioid use disorder. Complex patients with co-morbid pain and substance use disorders may benefit from referral to a specialist.

There are no standard opioid tapering schedules that are suitable for all patients. Good clinical practice dictates a patient-specific plan to taper the dose of the opioid gradually. For patients on NUCYNTA tablets who are physically opioid-dependent, initiate the taper by a small enough increment (e.g., no greater than 10% to 25% of the total daily dose) to avoid withdrawal symptoms, and proceed with dose-lowering at an interval of every 2 to 4 weeks. Patients who have been taking opioids for briefer periods of time may tolerate a more rapid taper.

It may be necessary to provide the patient with lower dosage strengths to accomplish a successful taper. Reassess the patient frequently to manage pain and withdrawal symptoms, should they emerge. Common withdrawal symptoms include restlessness, lacrimation, rhinorrhea, yawning, perspiration, chills, myalgia, and mydriasis. Other signs and symptoms also may develop, including irritability, anxiety, backache, joint pain, weakness, abdominal cramps, insomnia, nausea, anorexia, vomiting, diarrhea, or increased blood pressure, respiratory rate, or heart rate. If withdrawal symptoms arise, it may be necessary to pause the taper for a period of time or raise the dose of the opioid analgesic to the previous dose, and then proceed with a slower taper. In addition, evaluate patients for any changes in mood, emergence of suicidal thoughts, or use of other substances.

When managing patients taking opioid analgesics, particularly those who have been treated for an extended period of time and/or with high doses for chronic pain, ensure that a multimodal approach to pain management, including mental health support (if needed), is in place prior to initiating an opioid analgesic taper. A multimodal approach to pain management may optimize the treatment of chronic pain, as well as assist with the successful tapering of the opioid analgesic [see Warnings and Precautions (5.14), Drug Abuse and Dependence (9.3)].

3 DOSAGE FORMS AND STRENGTHS

Tablets: 50 mg, 75 mg, 100 mg.

50 mg: round, biconvex and film-coated yellow tablets with "O-M" on one side and "50" on the other side.

75 mg: round, biconvex and film-coated yellow-orange tablets with "O-M" on one side and "75" on the other side.

100 mg: round, biconvex and film-coated orange tablets with "O-M" on one side and "100" on the other side.

4 CONTRAINDICATIONS

NUCYNTA tablets are contraindicated in patients with:

- Significant respiratory depression [see Warnings and Precautions (5.2)]
- Acute or severe bronchial asthma in an unmonitored setting or in the absence of resuscitative equipment [see Warnings and Precautions (5.8)]
- Known or suspected gastrointestinal obstruction, including suspected paralytic ileus [see Warnings and Precautions (5.12)]
- Hypersensitivity to tapentadol (e.g., anaphylaxis, angioedema) or to any other ingredients of the product [see Adverse Reactions (6.2)]
- Concurrent use of monoamine oxidase inhibitors (MAOIs) or use of MAOIs within the last 14 days [see Drug Interactions (7)]

5 WARNINGS AND PRECAUTIONS

5.1 ADDICTION, ABUSE, AND MISUSE

NUCYNTA tablets contain tapentadol, a Schedule II controlled substance. As an opioid, NUCYNTA tablets exposes users to the risks of addiction, abuse, and misuse [see Drug Abuse and Dependence (9)].

Although the risk of addiction in any individual is unknown, it can occur in patients appropriately prescribed NUCYNTA tablets. Addiction can occur at recommended dosages and if the drug is misused or abused. The risk of opioid-related overdose or overdose-related death is increased with higher opioid doses, and this risk persists over the course of therapy. In postmarketing studies, addiction, abuse, misuse, and fatal and non-fatal opioid overdose were observed in patients with long-term opioid use [see Adverse Reactions (6.2)].

Assess each patient's risk for opioid addiction, abuse, or misuse prior to prescribing NUCYNTA tablets and reassess all patients receiving NUCYNTA tablets for the development of these behaviors and conditions. Risks are increased in patients with a personal or family history of substance abuse (including drug or alcohol abuse or addiction) or mental illness (e.g., major depression). The potential for these risks should not, however, prevent the proper management of pain in any given patient. Patients at increased risk may be prescribed opioids such as NUCYNTA tablets but use in such patients necessitates intensive counseling about the risks and proper use of NUCYNTA tablets along with frequent reevaluation for signs of addiction, abuse, and misuse. Consider recommending or prescribingan opioid overdose reversal agent[see Dosage and Administration (2.2), Warnings and Precautions (5.2)].

Opioids are sought for nonmedical use and are subject to diversion from legitimate prescribed use. Consider these risks when prescribing or dispensing NUCYNTA tablets. Strategies to reduce these risks include prescribing the drug in the smallest appropriate quantity and advising the patient on careful storage of the drug during the course of treatment and on the proper disposal of unused drug. Contact local state professional licensing board or state-controlled substances authority for information on how to prevent and detect abuse or diversion of this product.

5.2 LIFE-THREATENING RESPIRATORY DEPRESSION

Serious, life-threatening, or fatal respiratory depression has been reported with the use of opioids, even when used as recommended. Respiratory depression, if not immediately recognized and treated, may lead to respiratory arrest and death. Management of respiratory depression may include close observation, supportive measures, and use of opioid overdose reversal agents, depending on the patient's clinical status [see Overdosage (10)]. Carbon dioxide (CO2) retention from opioid-induced respiratory depression can exacerbate the sedating effects of opioids.

While serious, life-threatening, or fatal respiratory depression can occur at any time during the use of NUCYNTA tablets, the risk is greatest during the initiation of therapy or following a dosage increase.

To reduce the risk of respiratory depression, proper dosing and titration of NUCYNTA tablets are essential [see Dosage and Administration (2.3)]. Overestimating the NUCYNTA tablets dosage when converting patients from another opioid product can result in a fatal overdose with the first dose.

Accidental ingestion of even one dose of NUCYNTA tablets, especially by children, can result in respiratory depression and death due to an overdose of tapentadol.

Educate patients and caregivers on how to recognize respiratory depression and emphasize the importance of calling 911 or getting emergency medical help right away in the event of a known or suspected overdose.

Opioids can cause sleep-related breathing disorders including central sleep apnea (CSA) and sleep-related hypoxemia. Opioid use increases the risk of CSA in a dose-dependent fashion. In patients who present with CSA, consider decreasing the opioid dosage using best practices for opioid taper [see Dosage and Administration (2.6)].

Patient Access to an Opioid Overdose Reversal Agent for the Emergency Treatment of Opioid Overdose

Inform patients and caregivers about opioid overdose reversal agents (e.g., naloxone, nalmefene). Discuss the importance of having access to an opioid overdose reversal agent, especially if the patient has risk factors for overdose (e.g., concomitant use of CNS depressants, a history of opioid use disorder, or prior opioid overdose) or if there are household members (including children) or other close contacts at risk for accidental ingestion or opioid overdose. The presence of risk factors for overdose should not prevent the management of pain in any patient [see Warnings and Precautions (5.1, 5.3)].

Discuss the options for obtaining an opioid overdose reversal agent (e.g., prescription, over-the-counter, or as part of a community-based program). There are important differences among the opioid overdose reversal agents, such as route of administration, product strength, approved patient age range, and pharmacokinetics. Be familiar with these differences, as outlined in the approved labeling for those products, prior to recommending or prescribing such an agent.

Educate patients and caregivers on how to recognize respiratory depression, and how to use an opioid overdose reversal agent for the emergency treatment of opioid overdose. Emphasize the importance of calling 911 or getting emergency medical help, even if an opioid overdose reversal agent is administered [see Dosage and Administration (2.2), Warnings and Precautions (5.1, 5.3), Overdosage (10)].

5.3 RISKS FROM CONCOMITANT USE WITH BENZODIAZEPINES OR OTHER CNS DEPRESSANTS

Profound sedation, respiratory depression, coma, and death may result from the concomitant use of NUCYNTA tablets with benzodiazepines and/or other CNS depressants, including alcohol (e.g., non-benzodiazepine sedatives/hypnotics, anxiolytics, tranquilizers, muscle relaxants, general anesthetics, antipsychotics, gabapentinoids [gabapentin or pregabalin], and other opioids). Because of these risks, reserve concomitant prescribing of these drugs for use in patients for whom alternative treatment options are inadequate.

Observational studies have demonstrated that concomitant use of opioid analgesics and benzodiazepines increases the risk of drug-related mortality compared to use of opioid analgesics alone. Because of similar pharmacological properties, it is reasonable to expect similar risk with the concomitant use of other CNS depressant drugs with opioid analgesics [see Drug Interactions (7)].

If the decision is made to prescribe a benzodiazepine or other CNS depressant concomitantly with an opioid analgesic, prescribe the lowest effective dosages and minimum durations of concomitant use. In patients already receiving an opioid analgesic, prescribe a lower initial dose of the benzodiazepine or other CNS depressant than indicated in the absence of an opioid, and titrate based on clinical response. If an opioid analgesic is initiated in a patient already taking a benzodiazepine or other CNS depressant, prescribe a lower initial dose of the opioid analgesic, and titrate based on clinical response. Inform patients and caregivers of this potential interaction and educate them on the signs and symptoms of respiratory depression (including sedation).

If concomitant use is warranted, consider recommending or prescribing an opioid overdose reveral agent [see Dosage and Administration (2.2), Warnings and Precautions (5.2), Overdosage (10)].

Advise both patients and caregivers about the risks of respiratory depression and sedation when NUCYNTA tablets are used with benzodiazepines or other CNS depressants (including alcohol and illicit drugs). Advise patients not to drive or operate heavy machinery until the effects of concomitant use of the benzodiazepine or other CNS depressant have been determined. Screen patients for risk of substance use disorders, including opioid abuse and misuse, and warn them of the risk for overdose and death associated with the use of additional CNS depressants including alcohol and illicit drugs [see Drug Interactions (7)].

5.4 NEONATAL OPIOID WITHDRAWAL SYNDROME

Use of NUCYNTA tablets for an extended period of time during pregnancy can result in withdrawal in the neonate. Neonatal opioid withdrawal syndrome, unlike opioid withdrawal syndrome in adults, may be life-threatening if not recognized and treated, and requiresmanagement according to protocols developed by neonatology experts. Observe newborns for signs of neonatal opioid withdrawal syndrome and manage accordingly. Advise pregnant women using opioids for an extended period of time of the risk of neonatal opioid withdrawal syndrome and ensure that appropriate treatment will be available [see Use in Specific Populations (8.1)].

5.5 OPIOID ANALGESIC RISK EVALUATION AND MITIGATION STRATEGY (REMS)

To ensure that the benefits of opioid analgesics outweigh the risks of addiction, abuse, and misuse, the Food and Drug Administration (FDA) has required a Risk Evaluation and Mitigation Strategy (REMS) for these products. Under the requirements of the REMS, drug companies with approved opioid analgesic products must make REMS-compliant education programs available to healthcare providers. Healthcare providers are strongly encouraged to do all of the following:

- Complete a REMS-compliant education program offered by an accredited provider of continuing education (CE) or another education program that includes all the elements of the FDA Education Blueprint for Health Care Providers Involved in the Management or Support of Patients with Pain.
- Discuss the safe use, serious risks, and proper storage and disposal of opioid analgesics with patients and/or their caregivers every time these medicines are prescribed. The Patient Counseling Guide (PCG) can be obtained at this link: www.fda.gov/OpioidAnalgesicREMSPCG.
- Emphasize to patients and their caregivers the importance of reading the Medication Guide that they will receive from their pharmacist every time an opioid analgesic is dispensed to them.
- Consider using other tools to improve patient, household, and community safety, such as patient-prescriber agreements that reinforce patient-prescriber responsibilities.

To obtain further information on the opioid analgesic REMS and for a list of accredited REMS CME/CE, call 1-800-503-0784, or log on to www.opioidanalgesicrems.com. The FDA Blueprint can be found at www.fda.gov/OpioidAnalgesicREMSBlueprint.

5.6 OPIOID-INDUCED HYPERALGESIA AND ALLODYNIA

Opioid-Induced Hyperalgesia (OIH) occurs when an opioid analgesic paradoxically causes an increase in pain, or an increase in sensitivity to pain. This condition differs from tolerance, which is the need for increasing doses of opioids to maintain a defined effect [see Dependence (9.3)]. Symptoms of OIH include (but may not be limited to) increased levels of pain upon opioid dosage increase, decreased levels of pain upon opioid dosage decrease, or pain from ordinarily non-painful stimuli (allodynia). These symptoms may suggest OIH only if there is no evidence of underlying disease progression, opioid tolerance, opioid withdrawal, or addictive behavior.

Cases of OIH have been reported, both with short-term and longer-term use of opioid analgesics. Though the mechanism of OIH is not fully understood, multiple biochemical pathways have been implicated. Medical literature suggests a strong biologic plausibility between opioid analgesics and OIH and allodynia. If a patient is suspected to be experiencing OIH, carefully consider appropriately decreasing the dose of the current opioid analgesic or opioid rotation (safely switching the patient to a different opioid moiety) [see Dosage and Administration (2.7); Warnings and Precautions (5.13)].

5.7 SEROTONIN SYNDROME WITH CONCOMITANT USE OF SEROTONERGIC DRUGS

Cases of serotonin syndrome, a potentially life-threatening condition, have been reported during concomitant use of tapentadol with serotonergic drugs. Serotonergic drugs include selective serotonin reuptake inhibitors (SSRIs), serotonin and norepinephrine reuptake inhibitors (SNRIs), tricyclic antidepressants (TCAs), triptans, 5-HT3 receptor antagonists, drugs that affect the serotonergic neurotransmitter system (e.g., mirtazapine, trazodone, tramadol), certain muscle relaxants (i.e., cyclobenzaprine, metaxalone), and drugs that impair metabolism of serotonin (including monoamine oxidase inhibitors, both those intended to treat psychiatric disorders and also others, such as linezolid and intravenous methylene blue) [see Drug Interactions (7)]. This may occur within the recommended dosage range.

Serotonin syndrome symptoms may include mental-status changes (e.g., agitation, hallucinations, coma), autonomic instability (e.g., tachycardia, labile blood pressure, hyperthermia), neuromuscular aberrations (e.g., hyperreflexia, incoordination) and/or gastrointestinal symptoms (e.g., nausea, vomiting, diarrhea) and can be fatal. The onset of symptoms generally occurs within several hours to a few days of concomitant use but may occur later than that. Discontinue NUCYNTA tablets if serotonin syndrome is suspected.

5.8 LIFE-THREATENING RESPIRATORY DEPRESSION IN PATIENTS WITH CHRONIC PULMONARY DISEASE OR IN ELDERLY, CACHECTIC, OR DEBILITATED PATIENTS

The use of NUCYNTA tablets in patients with acute or severe bronchial asthma in an unmonitored setting or in the absence of resuscitative equipment is contraindicated.

Patients with Chronic Pulmonary Disease: NUCYNTA tablets-treated patients with significant chronic obstructive pulmonary disease or cor pulmonale, and those with a substantially decreased respiratory reserve, hypoxia, hypercapnia, or pre-existing respiratory depression are at increased risk of decreased respiratory drive including apnea, even at recommended dosages of NUCYNTA tablets [see Warnings and Precautions (5.2)].

Elderly, Cachectic, or Debilitated Patients: Life-threatening respiratory depression is more likely to occur in elderly, cachectic, or debilitated patients because they may have altered pharmacokinetics or altered clearance compared to younger, healthier patients [see Warnings and Precautions (5.2)].

Regularly evaluate such patients closely, particularly when initiating and titrating NUCYNTA tablets and when NUCYNTA tablets are given concomitantly with other drugs that depress respiration [see Warnings and Precautions (5.2, 5.3), Drug Interactions (7)]. Alternatively, consider the use of non-opioid analgesics in these patients.

5.9 ADRENAL INSUFFICIENCY

Cases of adrenal insufficiency have been reported with opioid use, more often following greater than one month of use. Presentation of adrenal insufficiency may include non-specific symptoms and signs including nausea, vomiting, anorexia, fatigue, weakness, dizziness, and low blood pressure. If adrenal insufficiency is suspected, confirm the diagnosis with diagnostic testing as soon as possible. If adrenal insufficiency is diagnosed, treat with physiologic replacement doses of corticosteroids. Wean the patient off of the opioid to allow adrenal function to recover and continue corticosteroid treatment until adrenal function recovers. Other opioids may be tried as some cases reported use of a different opioid without recurrence of adrenal insufficiency. The information available does not identify any particular opioids as being more likely to be associated with adrenal insufficiency.

5.10 SEVERE HYPOTENSION

NUCYNTA tablets may cause severe hypotension including orthostatic hypotension and syncope in ambulatory patients. There is increased risk in patients whose ability to maintain blood pressure has already been compromised by a reduced blood volume or concurrent administration of certain CNS depressant drugs (e.g., phenothiazines or general anesthetics) [see Drug Interactions (7)]. Regularly evaluate these patients for signs of hypotension after initiating or titrating the dosage of NUCYNTA tablets. In patients with circulatory shock, NUCYNTA tablets may cause vasodilation that can further reduce cardiac output and blood pressure. Avoid the use of NUCYNTA tablets in patients with circulatory shock.

5.11 RISKS OF USE IN PATIENTS WITH INCREASED INTRACRANIAL PRESSURE, BRAIN TUMORS, HEAD INJURY, OR IMPAIRED CONSCIOUSNESS

In patients who may be susceptible to the intracranial effects of CO2 retention (e.g., those with evidence of increased intracranial pressure or brain tumors), NUCYNTA tablets may reduce respiratory drive, and the resultant CO2 retention can further increase intracranial pressure.

Monitor such patients for signs of sedation and respiratory depression, particularly when initiating therapy with NUCYNTA tablets.

Opioids may also obscure the clinical course in a patient with a head injury. Avoid the use of NUCYNTA tablets in patients with impaired consciousness or coma.

5.12 RISKS OF GASTROINTESTINAL COMPLICATIONS

NUCYNTA tablets are contraindicated in patients with known or suspected gastrointestinal obstruction, including paralytic ileus.

The tapentadol in NUCYNTA tablets may cause spasm of the sphincter of Oddi. Opioids may cause increases in serum amylase. Regularly evaluate patients with biliary tract disease, including acute pancreatitis for worsening symptoms.

Cases of opioid-induced esophageal dysfunction (OIED) have been reported in patients taking opioids. The risk of OIED may increase as the dose and/or duration of opioids increases.

Regularly evaluate patients for signs and symptoms of OIED (e.g., dysphagia, regurgitation, non-cardiac chest pain) and, if necessary, adjust opioid therapy as clinically appropriate [see Clinical Pharmacology (12.2)].

5.13 INCREASED RISK OF SEIZURES IN PATIENTS WITH SEIZURE DISORDERS

The tapentadol in NUCYNTA tablets may increase the frequency of seizures in patients with seizure disorders, and may increase the risk of seizures occurring in other clinical settings associated with seizures. Regularly evaluate patients with a history of seizure disorders for worsened seizure control during NUCYNTA tablets therapy.

5.14 WITHDRAWAL

Do not rapidly reduce or abruptly discontinue NUCYNTA tablets in a patient physically dependent on opioids. When discontinuing NUCYNTA tablets in a physically dependent patient, gradually taper the dosage. Rapid tapering of tapentadol in a patient physically dependent on opioids may lead to a withdrawal syndrome and return of pain [see Dosage and Administration (2.7), Drug Abuse and Dependence (9.3)].

Additionally, avoid the use of mixed agonist/antagonist (e.g., pentazocine, nalbuphine, and butorphanol) or partial agonist (e.g., buprenorphine) analgesics in patients who are receiving a full opioid agonist analgesic, including NUCYNTA tablets. In these patients, mixed agonist/antagonist and partial agonist analgesics may reduce the analgesic effect and/or precipitate withdrawal symptoms [see Drug Interactions (7)].

5.15 RISKS OF DRIVING AND OPERATING MACHINERY

NUCYNTA tablets may impair the mental or physical abilities needed to perform potentially hazardous activities such as driving a car or operating machinery. Warn patients not to drive or operate dangerous machinery unless they are tolerant to the effects of NUCYNTA tablets and know how they will react to the medication.

5.16 INTERACTIONS WITH ALCOHOL, OTHER OPIOIDS, AND DRUGS OF ABUSE

Due to its mu-opioid agonist activity, NUCYNTA tablets may be expected to have additive effects when used in conjunction with alcohol, other opioids, or illicit drugs that cause central nervous system depression, respiratory depression, hypotension, and profound sedation, coma or death [see Drug Interactions (7)]. Instruct patients not to consume alcoholic beverages or use prescription or non-prescription products containing alcohol, other opioids, or drugs of abuse while on NUCYNTA tablets therapy [see Drug Interactions (7)].

5.17 RISK OF TOXICITY IN PATIENTS WITH HEPATIC IMPAIRMENT

A study with NUCYNTA tablets in subjects with hepatic impairment showed higher serum concentrations of tapentadol than in those with normal hepatic function. Avoid use of NUCYNTA tablets in patients with severe hepatic impairment. Reduce the dose of NUCYNTA tablets in patients with moderate hepatic impairment [see Dosage and Administration (2.4) and Clinical Pharmacology (12.3)]. Regularly evaluate patients with moderate hepatic impairment for respiratory and central nervous system depression when receiving NUCYNTA tablets.

5.18 RISK OF TOXICITY IN PATIENTS WITH RENAL IMPAIRMENT

Use of NUCYNTA tablets in patients with severe renal impairment is not recommended due to accumulation of a metabolite formed by glucuronidation of tapentadol. The clinical relevance of the elevated metabolite is not known [see Clinical Pharmacology (12.3)].

6 ADVERSE REACTIONS

The following adverse reactions are discussed, or described in greater detail, in other sections:

- Addiction, Abuse, and Misuse [see Warnings and Precautions (5.1)]
- Life-Threatening Respiratory Depression [see Warnings and Precautions (5.2)]
- Interactions with Benzodiazepine or Other CNS Depressants [see Warnings and Precautions (5.3)]
- Neonatal Opioid Withdrawal Syndrome [see Warnings and Precautions (5.4)]
- Opioid-Induced Hyperalgesia and Allodynia [see Warnings and Precautions (5.6)
- Serotonin Syndrome [see Warnings and Precautions (5.7)]
- Adrenal Insufficiency [see Warnings and Precautions (5.9)]
- Severe Hypotension [see Warnings and Precautions (5.10)]
- Gastrointestinal Adverse Reactions [see Warnings and Precautions (5.12)]
- Seizures [see Warnings and Precautions (5.13)]
- Withdrawal [see Warnings and Precautions (5.14)]

6.1 CLINICAL TRIALS EXPERIENCE

Adults

Because clinical trials are conducted under widely varying conditions, adverse reaction rates observed in the clinical trials of a drug cannot be directly compared to rates in the clinical trials of another drug and may not reflect the rates observed in practice.

Based on data from nine Phase 2/3 studies that administered multiple doses (seven placebo- and/or active-controlled, one noncontrolled and one Phase 3 active-controlled safety study) the most common adverse reactions (reported by ≥10% in any NUCYNTA tablets dose group) were: nausea, dizziness, vomiting and somnolence.

The most common reasons for discontinuation due to adverse reactions in the studies described above (reported by ≥1% in any NUCYNTA tablets dose group) were dizziness (2.6% vs. 0.5%), nausea (2.3% vs. 0.6%), vomiting (1.4% vs. 0.2%), somnolence (1.3% vs. 0.2%) and headache (0.9% vs. 0.2%) for NUCYNTA- and placebo-treated patients, respectively.

Seventy-six percent of NUCYNTA-treated patients from the nine studies experienced adverse events.

NUCYNTA tablets were studied in multiple-dose, active- or placebo-controlled studies, or noncontrolled studies (n = 2178), in single-dose studies (n = 870), in open-label study extension (n = 483) and in Phase 1 studies (n = 597). Of these, 2034 patients were treated with doses of 50 mg to 100 mg of NUCYNTA tablets dosed every 4 to 6 hours.

The data described below reflect exposure to NUCYNTA tablets in 3161 patients, including 449 exposed for 45 days. NUCYNTA tablets were studied primarily in placebo- and active-controlled studies (n = 2266, and n = 2944, respectively). The population was 18 to 85 years old (mean age 46 years), 68% were female, 75% white and 67% were postoperative. Most patients received NUCYNTA tablets doses of 50 mg, 75 mg, or 100 mg every 4 to 6 hours.

Table 1. Adverse Reactions Reported by ≥1% of NUCYNTA-Treated Patients In Seven Phase 2/3 Placebo- and/or Oxycodone-Controlled, One Non-controlled, and One Phase 3 Oxycodone-Controlled Safety, Multiple-Dose Clinical Studies
System/Organ Class MedDRA Preferred Term | NUCYNTA 21 mg – 120 mg (n = 2178) % | Placebo (n = 619) %
Gastrointestinal disorders
Nausea | 30 | 13
Vomiting | 18 | 4
Constipation | 8 | 3
Dry mouth | 4 | <1
Dyspepsia | 2 | <1
General disorders and administration site conditions
Fatigue | 3 | <1
Feeling hot | 1 | <1
Infections and infestations
Nasopharyngitis | 1 | <1
Upper respiratory tract infection | 1 | <1
Urinary tract infection | 1 | <1
Metabolism and nutrition disorders
Decreased appetite | 2 | 0
Nervous system disorders
Dizziness | 24 | 8
Somnolence | 15 | 3
Tremor | 1 | <1
Lethargy | 1 | <1
Psychiatric disorders
Insomnia | 2 | <1
Confusional state | 1 | 0
Abnormal dreams | 1 | <1
Anxiety | 1 | <1
Skin and subcutaneous tissue disorders
Pruritus | 5 | 1
Hyperhidrosis | 3 | <1
Pruritus generalized | 3 | <1
Rash | 1 | <1
Vascular disorders
Hot flush | 1 | <1

The following adverse drug reactions occurred in less than 1% of NUCYNTA-treated patients in the pooled safety data from nine Phase 2/3 clinical studies:

Cardiac disorders: heart rate increased, heart rate decreased

Eye disorders: visual disturbance

Gastrointestinal disorders: abdominal discomfort, impaired gastric emptying

General disorders and administration site conditions: irritability, edema, drug withdrawal syndrome, feeling drunk

Immune system disorders: hypersensitivity

Investigations: gamma-glutamyltransferase increased, alanine aminotransferase increased, aspartate aminotransferase increased

Musculoskeletal and connective tissue disorders: involuntary muscle contractions, sensation of heaviness

Nervous system disorders: hypoesthesia, paresthesia, disturbance in attention, sedation, dysarthria, depressed level of consciousness, memory impairment, ataxia, presyncope, syncope, coordination abnormal, seizure

Psychiatric disorders: euphoric mood, disorientation, restlessness, agitation, nervousness, thinking abnormal

Renal and urinary disorders: urinary hesitation, pollakiuria

Respiratory, thoracic and mediastinal disorders: oxygen saturation decreased, cough, dyspnea, respiratory depression

Skin and subcutaneous tissue disorders: urticaria

Vascular disorders: blood pressure decreased

In the pooled safety data, the overall incidence of adverse reactions increased with increased dose of NUCYNTA tablets, as did the percentage of patients with adverse reactions of nausea, dizziness, vomiting, somnolence, and pruritus.

Clinical Trial Experience in Pediatric Patients from Birth to 17 Years of Age

The safety of NUCYNTA (tapentadol) tablets is based on studies using NUCYNTA (tapentadol) oral solution. The safety of NUCYNTA (tapentadol) oral solution was evaluated in 248 pediatric patients, birth to 17 years of age. One hundred twenty-nine (129) patients with moderate to severe acute pain from a surgical procedure were treated with a single dose of NUCYNTA (tapentadol) oral solution. One hundred nineteen (119) patients who had undergone surgery that, in the investigator's opinion, would reliably produce moderate to severe pain requiring opioid treatment were treated with multiple doses of NUCYNTA (tapentadol) oral solution. The most common reasons for discontinuation from treatment due to adverse reactions in the multiple dose study were nausea (1.9%), somnolence (1.9%) and vomiting (1.3%). The most common adverse reactions in patients 6 years and older in the multiple-dose study were vomiting (24.7%), constipation (16.5%), nausea (10.6%), pruritus (9.4%), and pyrexia (5.9%).

6.2 POST-MARKETING EXPERIENCE

The following additional adverse reactions have been identified during post approval use of tapentadol. Because these reactions are reported voluntarily from a population of uncertain size, it is not always possible to reliably estimate their frequency or establish a causal relationship to drug exposure.

Gastrointestinal disorders: diarrhea

Nervous system disorders: headache

Psychiatric disorders: hallucination, suicidal ideation, panic attack

Cardiac disorders: palpitations

Serotonin syndrome: Cases of serotonin syndrome, a potentially life-threatening condition, have been reported during concomitant use of opioids with serotonergic drugs.

Adrenal insufficiency: Cases of adrenal insufficiency have been reported with opioid use, more often following greater than one month of use.

Anaphylaxis: Anaphylaxis has been reported with ingredients contained in NUCYNTA tablets.

Androgen deficiency: Cases of androgen deficiency have occurred with chronic use of opioids for an extended period of time [see Clinical Pharmacology (12.2)].

Hyperalgesia and Allodynia: Cases of hyperalgesia and allodynia have been reported with opioid therapy of any duration [see Warnings and Precautions (5.5)]

Hypoglycemia: Cases of hypoglycemia have been reported in patients taking opioids. Most reports were in patients with at least one predisposing risk factor (e.g., diabetes).

Opioid-induced esophageal dysfunction (OIED): Cases of OIED have been reported in patients taking opioids and may occur more frequently in patients taking higher doses of opioidsopioid, and/or in patients taking opioids longer term [see Warnings and Precautions (5.12)].

Adverse Reactions from Observational Studies

A prospective, observational cohort study estimated the risks of addiction, abuse, and misuse in patients initiating long-term use of Schedule II opioid analgesics between 2017 and 2021. Study participants included in one or more analyses had been enrolled in selected insurance plans or health systems for at least one year, were free of at least one outcome at baseline, completed a minimum number of follow-up assessments, and either: 1) filled multiple extended-release/long-acting opioid analgesic prescriptions during a 90-day period (n=978); or 2) filled any Schedule II opioid analgesic prescriptions covering at least 70 of 90 days (n=1,244). Those included also had no dispensing of the qualifying opioids in the previous 6 months.

Over 12 months:

- approximately 1% to 6% of participants across the two cohorts newly met criteria for addiction, as assessed with two validated interview based measures of moderate-to-severe opioid use disorder based on Diagnostic and Statistical Manual of Mental Disorders, Fifth Edition (DSM-5) criteria, and
- approximately 9% and 22% of participants across the two cohorts newly met criteria for prescription opioid abuse and misuse [defined in Drug Abuse and Dependence (9.2)], respectively, as measured with a validated self-reported instrument.

A retrospective, observational cohort study estimated the risk of opioid involved overdose or opioid overdose-related death in patients with new long-term use of Schedule II opioid analgesics from 2006 through 2016 (n=220,249). Included patients had been enrolled in either one of two commercial insurance programs, one managed care program, or one Medicaid program for at least 9 months. New long-term use was defined as having Schedule II opioid analgesic prescriptions covering at least 70 days' supply over the 3 months prior to study entry and none during the preceding 6 months. Patients were excluded if they had an opioid-involved overdose in the 9 months prior to study entry. Overdose was measured using a validated medical code-based algorithm with linkage to the National Death Index database. The 5-year cumulative incidence estimates for opioid-involved overdose or opioid overdose-related death ranged from approximately 1.5% to 4% across study sites, counting only the first event during follow-up. Approximately 17% of first opioid overdoses observed over the entire study period (5-11 years, depending on the study site) were fatal. Higher baseline opioid dose was the strongest and most consistent predictor of opioid-involved overdose or opioid overdose-related death. Study exclusion criteria may have selected patients at lower risk of overdose, and substantial loss to follow-up (approximately 80%) also may have biased estimates.

The risk estimates from the studies described above may not be generalizable to all patients receiving opioid analgesics, such as those with exposures shorter or longer than the duration evaluated in the studies.

7 DRUG INTERACTIONS

Table 2 includes clinically significant drug interactions with NUCYNTA tablets.

Table 2. Clinically Significant Drug Interactions with NUCYNTA Tablets
Benzodiazepines and other Central Nervous System (CNS) Depressants
Clinical Impact: | Due to additive pharmacologic effect, the concomitant use of benzodiazepines or other CNS depressants including alcohol, increases the risk of respiratory depression, profound sedation, coma, and death [Warnings and Precautions (5.3)].
Intervention: | Reserve concomitant prescribing of these drugs for use in patients for whom alternative treatment options are inadequate. Limit dosages and durations to the minimum required. Inform patients and caregivers of this potential interaction and educate them on the signs and symptoms of respiratory depression (including sedation). If concomitant use is warranted, consider recommending or prescribing an opioid overdose reversal agent [see Dosage and Administration (2.2), Warnings and Precautions (5.1, 5.2, 5.3)].
Examples: | Benzodiazepines and other sedatives/hypnotics, anxiolytics, tranquilizers, muscle relaxants, general anesthetics, antipsychotics, gabapentinoids (gabapentin or pregabalin), other opioids, alcohol.
Serotonergic Drugs
Clinical Impact: | The concomitant use of opioids with other drugs that affect the serotonergic neurotransmitter system has resulted in serotonin syndrome [see Warnings and Precautions (5.7)].
Intervention: | If concomitant use is warranted, frequently evaluate the patient, particularly during treatment initiation and dose adjustment. Discontinue NUCYNTA tablets if serotonin syndrome is suspected.
Examples: | Selective serotonin reuptake inhibitors (SSRIs), serotonin and norepinephrine reuptake inhibitors (SNRIs), tricyclic antidepressants (TCAs), triptans, 5-HT3 receptor antagonists, drugs that affect the serotonin neurotransmitter system (e.g., mirtazapine, trazodone, tramadol), certain muscle relaxants (i.e., cyclobenzaprine, metaxalone), monoamine oxidase inhibitors (those intended to treat psychiatric disorders and also others, such as linezolid and intravenous methylene blue).
Monoamine Oxidase Inhibitors (MAOIs)
Clinical Impact: | MAOI interactions with opioids may manifest as serotonin syndrome or opioid toxicity (e.g., respiratory depression, coma) [see Warnings and Precautions (5.3)]
Intervention: | Do not use NUCYNTA tablets in patients taking MAOIs or within 14 days of stopping such treatment. If urgent use of an opioid is necessary, use test doses and frequent titration of small doses of other opioids (such as oxycodone, hydrocodone, oxymorphone, hydrocodone, or buprenorphine) to treat pain while closely monitoring blood pressure and signs and symptoms of CNS and respiratory depression.
Examples: | phenelzine, tranylcypromine, linezolid
Mixed Agonist/Antagonist and Partial Agonist Opioid Analgesics
Clinical Impact: | May reduce the analgesic effect of NUCYNTA tablets and/or precipitate withdrawal symptoms.
Intervention: | Avoid concomitant use.
Examples: | butorphanol, nalbuphine, pentazocine, buprenorphine
Muscle Relaxants
Clinical Impact: | Tapentadol may enhance the neuromuscular blocking action of skeletal muscle relaxants and produce an increased degree of respiratory depression.
Intervention: | Because respiratory depression may be greater than otherwise expected, decrease the dosage of NUCYNTA tablets and/or the muscle relaxant as necessary. Due to the risk of respiratory depression with concomitant use of skeletal muscle relaxants and opioids, consider recommending or prescribing an opioid overdose reversal agent [see Dosage and Administration (2.2), Warnings and Precautions (5.2, 5.3)]
Examples: | cyclobenzaprine, metaxalone
Diuretics
Clinical Impact: | Opioids can reduce the efficacy of diuretics by inducing the release of antidiuretic hormone.
Intervention: | Evaluate patients for signs of diminished diuresis and/or effects on blood pressure and increase the dosage of the diuretic as needed.
Anticholinergic Drugs
Clinical Impact: | The concomitant use of anticholinergic drugs may increase risk of urinary retention and/or severe constipation, which may lead to paralytic ileus.
Intervention: | Evaluate patients for signs of urinary retention or reduced gastric motility when NUCYNTA tablets is used concomitantly with anticholinergic drugs.
Alcohol, Other Opioids, and Drugs of Abuse
Clinical Impact: | Due to its mu-opioid agonist activity, NUCYNTA tablets may be expected to have additive effects when used in conjunction with alcohol, other opioids, or illicit drugs that cause central nervous system depression, respiratory depression, hypotension, and profound sedation, coma or death [see Warnings and Precautions (5.16)].
Intervention: | Instruct patients not to consume alcoholic beverages or use prescription or non- prescription products containing alcohol, other opioids, or drugs of abuse while on NUCYNTA tablets therapy.
Examples: | Alcohol, other opioids, illicit drugs

8 USE IN SPECIFIC POPULATIONS

8.1 Pregnancy

Risk Summary

Use of opioid analgesics for an extended period of time during pregnancy may cause neonatal opioid withdrawal syndrome [see Warnings and Precautions (5.4)]. Available data with NUCYNTA tablets are insufficient to inform a drug-associated risk for major birth defects and miscarriage or adverse maternal outcomes. There are risks to the mother and infant associated with use of NUCYNTA tablets for an extended period of time during pregnancy (see Clinical Considerations).

In animal reproduction studies, embryofetal mortality and structural malformations were observed with subcutaneous administration of tapentadol during organogenesis to rabbits and delays in skeletal maturation were observed in rats at exposures equivalent to and less than the maximum recommended human dose (MRHD), respectively. When administered to pregnant rats during organogenesis and through lactation, increased pup mortality was noted following oral tapentadol exposures to doses equivalent to the MRHD [see Data].

Based on animal data, advise pregnant women of the potential risk to a fetus.

The background risk of major birth defects and miscarriage for the indicated population is unknown. All pregnancies have a background risk of birth defect, loss, or other adverse reaction. In the U.S. general population, the estimated background risk of major birth defects and miscarriage in clinically recognized pregnancies is 2-4% and 15-20%, respectively.

Clinical Considerations

Fetal/Neonatal Adverse Reactions

Use of opioid analgesics for an extended period of time during pregnancy for medical or nonmedical purposes can result in physical dependence in the neonate and neonatal opioid withdrawal syndrome shortly after birth.

Neonatal opioid withdrawal syndrome presents as irritability, hyperactivity and abnormal sleep pattern, high pitched cry, tremor, vomiting, diarrhea and failure to gain weight. The onset, duration, and severity of neonatal opioid withdrawal syndrome vary based on the specific opioid used, duration of use, timing and amount of last maternal use, and rate of elimination of the drug by the newborn. Observe newborns for symptoms of neonatal opioid withdrawal syndrome and manage accordingly [see Warnings and Precautions (5.4)].

Labor or Delivery

Opioids cross the placenta and may produce respiratory depression and psycho-physiologic effects in neonates. An opioid overdose reversal agent, such as naloxone or nalmefene, must be available for reversal of opioid-induced respiratory depression in the neonate. NUCYNTA tablets are not recommended for use in pregnant women during or immediately prior to labor, when other analgesic techniques are more appropriate. Opioid analgesics, including NUCYNTA tablets, can prolong labor through actions which temporarily reduce the strength, duration, and frequency of uterine contractions. However, this effect is not consistent and may be offset by an increased rate of cervical dilation, which tends to shorten labor. Monitor neonates exposed to opioid analgesics during labor for signs of excess sedation and respiratory depression.

Data

Animal Data

Tapentadol HCl was evaluated for teratogenic effects in pregnant rats and rabbits following subcutaneous exposure during organogenesis. When tapentadol was administered twice daily by the subcutaneous route in rats at dose levels of 10, 20, or 40 mg/kg/day [producing up to 1 times the plasma exposure at the maximum recommended human dose (MRHD) of 700 mg/day based on an area under the time-curve (AUC) comparison], no teratogenic effects were observed.

Evidence of embryofetal toxicity included transient delays in skeletal maturation (i.e. reduced ossification) at the 40 mg/kg/day dose which was associated with significant maternal toxicity.

Administration of tapentadol HCl in rabbits at doses of 4, 10, or 24 mg/kg/day by subcutaneous injection [producing 0.2, 0.6, and 1.85 times the plasma exposure at the MRHD based on an AUC comparison] revealed embryofetal toxicity at doses ≥10 mg/kg/day. Findings included reduced fetal viability, skeletal delays and other variations. In addition, there were multiple malformations including gastroschisis/thoracogastroschisis, amelia/phocomelia, and cleft palate at doses ≥10 mg/kg/day and above, and ablepharia, encephalopathy, and spina bifida at the high dose of 24 mg/kg/day. Embryofetal toxicity, including malformations, may be secondary to the significant maternal toxicity observed in the study.

In a study of pre- and postnatal development in rats, oral administration of tapentadol at doses of 20, 50, 150, or 300 mg/kg/day to pregnant and lactating rats during the late gestation and early postnatal period [resulting in up to 1.7 times the plasma exposure at the MRHD on an AUC basis] did not influence physical or reflex development, the outcome of neurobehavioral tests or reproductive parameters. Treatment-related developmental delay was observed, including incomplete ossification, and significant reductions in pup body weights and body weight gains at doses associated with maternal toxicity (150 mg/kg/day and above). At maternal tapentadol doses ≥150 mg/kg/day, a dose-related increase in pup mortality was observed through postnatal Day 4.

8.2 Lactation

Risk Summary

There are no data on the presence of tapentadol in human milk, the effects on the breastfed infant, or the effects on milk production. Tapentadol is present in animal milk. When a drug is present in animal milk, it is likely that the drug will be present in human milk. Infants exposed to NUCYNTA tablets through breast milk should be monitored for excess sedation and respiratory depression. Withdrawal symptoms can occur in breastfed infants when maternal administration of an opioid analgesic is stopped, or when breastfeeding is stopped.

The developmental and health benefits of breastfeeding should be considered along with the mother's clinical need for NUCYNTA tablets and any potential adverse effects on the breastfed infant from NUCYNTA tablets or from the underlying maternal condition.

8.3 Females and Males of Reproductive Potential

Infertility

Use of opioids for an extended period of time may cause reduced fertility in females and males of reproductive potential. It is not known whether these effects on fertility are reversible [see Adverse Reactions (6.2), Clinical Pharmacology (12.2)].

8.4 Pediatric use

The safety and effectiveness of NUCYNTA (tapentadol) tablets in pediatric patients ages 6 years and older who weigh at least 40 kg have been established. Use of NUCYNTA (tapentadol) tablets in pediatric patients ages 6 years and older who weigh at least 40 kg is based on one randomized, double-blind, placebo-controlled, multiple-dose efficacy and safety study of NUCYNTA (tapentadol) oral solution in 175 pediatric patients from birth to 17 years of age who had undergone surgery that would reliably produce moderate to severe pain and supported by pharmacokinetic and safety data from three open-label, single-dose studies of NUCYNTA (tapentadol) oral solution in 129 patients from birth to 17 years of age with moderate to severe acute pain from a surgical procedure [see Clinical Studies (14.2)].

The safety and effectiveness of NUCYNTA (tapentadol) tablets in pediatric patients less than 6 years of age have not been established. In pediatric patients less than 6 years of age, NUCYNTA (tapentadol) oral solution did not demonstrate efficacy compared to placebo when evaluated in one randomized, double-blind, placebo-controlled, multiple-dose study in 175 pediatric patients from birth to 17 years of age who had undergone surgery that would reliably produce moderate to severe pain [see Clinical Studies (14.2)].

The safety and effectiveness of NUCYNTA (tapentadol) tablets in pediatric patients who weigh less than 40 kg have not been established because the recommended dosage cannot be achieved with available tablet strengths. Consider use of another NUCYNTA product, such as NUCYNTA (tapentadol) oral solution, in patients who cannot swallow oral tablets or who weigh less than 40 kg [see Dosage and Administration (2.3)].

NUCYNTA (tapentadol) tablets have not been studied in pediatric patients with hepatic or renal impairment; therefore, use in these populations is not recommended [see Dosage and Administration (2.4)].

8.5 Geriatric use

Of the total number of patients in Phase 2/3 double-blind, multiple-dose clinical studies of NUCYNTA tablets, 19% were 65 and over, while 5% were 75 and over. No overall differences in effectiveness were observed between these patients and younger patients. The rate of constipation was higher in subjects greater than or equal to 65 years than those less than 65 years (12% vs. 7%).

Elderly patients (aged 65 years or older) may have increased sensitivity to tapentadol. In general, use caution when selecting a dosage for an elderly patient, usually starting at the low end of the dosing range, reflecting the greater frequency of decreased hepatic, renal, or cardiac function and of concomitant disease or other drug therapy.

Respiratory depression is the chief risk for elderly patients treated with opioids, and has occurred after large initial doses were administered to patients who were not opioid-tolerant or when opioids were co-administered with other agents that depress respiration. Titrate the dosage of NUCYNTA tablets slowly in geriatric patients and frequently reevaluate the patient for signs of central nervous system and respiratory depression [see Warnings and Precautions (5.2)].

Tapentadol is known to be substantially excreted by the kidney, and the risk of adverse reactions to this drug may be greater in patients with impaired renal function. Because elderly patients are more likely to have decreased renal function, care should be taken in dose selection, and it may be useful to regularly evaluate renal function.

8.6 Hepatic impairment

Administration of tapentadol resulted in higher exposures and serum levels of tapentadol in subjects with impaired hepatic function compared to subjects with normal hepatic function [see Clinical Pharmacology (12.3)]. Use of NUCYNTA tablets are not recommended in patients with severe hepatic impairment (Child-Pugh Score 10 to 15) [see Warnings and Precautions (5.17)]. The dose of NUCYNTA tablets should be reduced in patients with moderate hepatic impairment (Child-Pugh Score 7 to 9) [see Dosage and Administration (2.5)]. No dosage adjustment is recommended in patients with mild hepatic impairment (Child-Pugh Score 5 to 6) [see Warnings and Precautions (5.17), Clinical Pharmacology (12.3)].

8.7 Renal impairment

Use of NUCYNTA tablets in patients with severe renal impairment (creatinine clearance less than 30 mL/minute) is not recommended. No dosage adjustment is recommended in patients with mild or moderate renal impairment (creatinine clearance 30-90 mL/minute) [see Warnings and Precautions (5.18), Clinical Pharmacology (12.1)].

9 DRUG ABUSE AND DEPENDENCE

9.1 CONTROLLED SUBSTANCE

NUCYNTA tablets contain tapentadol, a Schedule II controlled substance.

9.2 ABUSE

NUCYNTA tablets contain tapentadol, a substance with high potential for misuse and abuse, which can lead to the development of substance use disorder, including addiction [see Warnings and Precautions (5.1)].

Misuse is the intentional use, for therapeutic purposes, of a drug by an individual in a way other than prescribed by a healthcare provider or for whom it was not prescribed.

Abuse is the intentional, non-therapeutic use of a drug, even once, for its desirable psychological or physiological effects.

Drug addiction is a cluster of behavioral, cognitive, and physiological phenomena that may include a strong desire to take the drug, difficulties in controlling drug use (e.g., continuing drug use despite harmful consequences, giving a higher priority to drug use than other activities and obligations), and possible tolerance or physical dependence.

Misuse and abuse of NUCYNTA tablets increase risk of overdose, which may lead to central nervous system and respiratory depression, hypotension, seizures, and death. The risk is increased with concurrent abuse of NUCYNTA tablets with alcohol and/or other CNS depressants. Abuse of and addiction to opioids in some individuals may not be accompanied by concurrent tolerance and symptoms of physical dependence. In addition, abuse of opioids can occur in the absence of addiction.

All patients treated with opioids require careful and frequent reevaluation for signs of misuse, abuse, and addiction, because use of opioid analgesic products carries the risk of addiction even under appropriate medical use. Patients at high risk of NUCYNTA tablet abuse include those with a history of prolonged use of any opioid, including products containing tapentadol, those with a history of drug or alcohol abuse, or those who use NUCYNTA tablets in combination with other abused drugs.

"Drug-seeking" behavior is very common in persons with substance use disorders. Drug-seeking tactics include emergency calls or visits near the end of office hours, refusal to undergo appropriate examination, testing, or referral, repeated "loss" of prescriptions, tampering with prescriptions, and reluctance to provide prior medical records or contact information for other treating healthcare provider(s). "Doctor shopping" (visiting multiple prescribers to obtain additional prescriptions) is common among people who abuse drugs and people with substance use disorder. Preoccupation with achieving adequate pain relief can be appropriate behavior in a patient with inadequate pain control.

NUCYNTA tablets, like other opioids, can be diverted for nonmedical use into illicit channels of distribution. Careful record-keeping of prescribing information, including quantity, frequency, and renewal requests, as required by state and federal law, is strongly advised.

Proper assessment of the patient, proper prescribing practices, periodic reevaluation of therapy, and proper dispensing and storage are appropriate measures that help to limit abuse of opioid drugs.

Risks Specific to Abuse of NUCYNTA Tablets

Abuse of NUCYNTA tablets pose a risk of overdose and death. The risk is increased with concurrent use of NUCYNTA tablets with alcohol and/or other central nervous system depressants.

NUCYNTA tablets are approved for oral use only.

Parenteral drug abuse is commonly associated with transmission of infectious diseases such as hepatitis and HIV.

9.3 DEPENDENCE

Both tolerance and physical dependence can develop during use of opioid therapy.

Tolerance is a physiological state characterized by a reduced response to a drug after repeated administration (i.e., a higher dose of a drug is required to produce the same effect that was once obtained at a lower dose).

Physical dependence is a state that develops as a result of a physiological adaptation in response to repeated drug use, manifested by withdrawal signs and symptoms after abrupt discontinuation or a significant dose reduction of a drug.

Withdrawal may be precipitated through the administration of drugs with opioid antagonist activity (e.g., naloxone, nalmefene), mixed agonist/antagonist analgesics (e.g., pentazocine, butorphanol, nalbuphine), or partial agonists (e.g., buprenorphine). Physical dependence may not occur to a clinically significant degree until after several days to weeks of continued use.

Do not rapidly reduce or abruptly discontinue NUCYNTA tablets in a patient physically dependent on opioids. Rapid reduction or abruptly discontinuation of NUCYNTA tablets in a patient physically dependent on opioids may lead to serious withdrawal symptoms, uncontrolled pain, and suicide. Rapid discontinuation has also been associated with attempts to find other sources of opioid analgesics, which may be confused with drug-seeking for abuse.

When discontinuing NUCYNTA tablets, gradually taper the dosage using a patient-specific plan that considers the following: the dose of NUCYNTA tablets the patient has been taking, the duration of treatment, and the physical and psychological attributes of the patient. To improve the likelihood of a successful taper and minimize withdrawal symptoms, it is important that the opioid tapering schedule is agreed upon by the patient. In patients taking opioids for an extended period of time at high doses, ensure that a multimodal approach to pain management, including mental health support (if needed), is in place prior to initiating an opioid analgesic taper [see Dosage and Administration (2.7), and Warnings and Precautions (5.13)].

Infants born to mothers physically dependent on opioids will also be physically dependent and may exhibit respiratory difficulties and withdrawal signs [see Use in Specific Populations (8.1)].

10 OVERDOSAGE

Clinical Presentation

Acute overdosage with tapentadol can be manifested by respiratory depression, somnolence progressing to stupor or coma, skeletal muscle flaccidity, cold and clammy skin, constricted pupils, and, in some cases, pulmonary edema, bradycardia, hypotension, hypoglycemia, partial or complete airway obstruction, atypical snoring, and death. Marked mydriasis rather than miosis may be seen due to severe hypoxia in overdose situations [see Clinical Pharmacology (12.2)].

Toxic leukoencephalopathy has been reported after opioid overdose and can present hours, days, or weeks after apparent recovery from the initial intoxication.

Treatment of Overdose

In case of overdose, priorities are the reestablishment of a patent and protected airway and institution of assisted or controlled ventilation if needed. Employ other supportive measures (including oxygen and vasopressors) in the management of circulatory shock and pulmonary edema as indicated. Cardiac arrest or arrhythmias will require advanced life support measures.

For clinically significant respiratory or circulatory depression secondary to opioid overdose, administer an opioid overdose reversal agent such as naloxone or nalmefene.

Because the duration of opioid reversal is expected to be less than the duration of action of tapentadol in NUCYNTA tablets, carefully monitor the patient until spontaneous respiration is reliably reestablished. If the response to an opioid overdose reversal agent is suboptimal or only brief in nature, administer additional reversal agent as directed in the product's prescribing information.

In an individual physically dependent on opioids, administration of the recommended usual dosage of the opioid reversal agent will precipitate an acute withdrawal syndrome. The severity of the withdrawal symptoms experienced will depend on the degree of physical dependence and the dose of the reversal agent administered. If a decision is made to treat serious respiratory depression in the physically dependent patient, administration of the reversal agent should be begun with care and by titration with smaller than usual doses of the reversal agent.

11 DESCRIPTION

NUCYNTA (tapentadol) tablets are a mu-opioid receptor agonist, available in immediate-release film-coated tablets for oral administration, containing 58.24, 87.36 and 116.48 mg of tapentadol hydrochloride in each tablet strength, equivalent to 50, 75, and 100 mg of tapentadol free-base, respectively. The chemical name is 3-[(1R,2R)-3-(dimethylamino)-1-ethyl-2-methylpropyl]phenol monohydrochloride, and it has the following chemical structure:

The molecular weight of tapentadol HCl is 257.80, and the molecular formula is C14H23NO∙HCl. The n-octanol:water partition coefficient log P value is 2.87. The pKa values are 9.34 and 10.45.

The inactive ingredients in NUCYNTA tablets include: croscarmellose sodium, lactose monohydrate, magnesium stearate, microcrystalline cellulose, povidone. The film coatings for all tablet strengths contain polyvinyl alcohol, titanium dioxide, polyethylene glycol, talc, and the colorant FD&C Yellow #6 aluminum lake; the film coatings for the 50 mg and 75 mg tablets also contain the additional colorant D&C Yellow #10 aluminum lake.

12 CLINICAL PHARMACOLOGY

12.1 MECHANISM OF ACTION

Tapentadol is a centrally-acting synthetic analgesic. The exact mechanism of action is unknown. Although the clinical relevance is unclear, preclinical studies have shown that tapentadol is a mu-opioid receptor (MOR) agonist and a norepinephrine reuptake inhibitor (NRI). Analgesia in animal models is derived from both of these properties.

12.2 PHARMACODYNAMICS

Effects on the Central Nervous System

Tapentadol produces respiratory depression by direct action on the brainstem respiratory centers. The respiratory depression involves a reduction in the responsiveness of the brain stem respiratory centers to both increases in carbon dioxide tension and electrical stimulation.

Tapentadol causes miosis, even in total darkness. Pinpoint pupils are a sign of opioid overdose but are not pathognomonic (e.g., pontine lesions of hemorrhagic or ischemic origin may produce similar findings). Marked mydriasis rather than miosis may be seen with hypoxia in overdose situations.

Effects on the Gastrointestinal Tract and Other Smooth Muscle

Tapentadol causes a reduction in motility associated with an increase in smooth muscle tone in the antrum of the stomach and duodenum. Digestion of food in the small intestine is delayed and propulsive contractions are decreased. Propulsive peristaltic waves in the colon are decreased, while tone may be increased to the point of spasm, resulting in constipation. Other opioid- induced effects may include a reduction in biliary and pancreatic secretions, spasm of sphincter of Oddi, and transient elevations in serum amylase, and opioid-induced esophageal dysfunction (OIED).

Effects on the Cardiovascular System

There was no effect of therapeutic and supratherapeutic doses of tapentadol on the QT interval. In a randomized, double-blind, placebo- and positive-controlled crossover study, healthy subjects were administered five consecutive doses of NUCYNTA 100 mg every 6 hours, NUCYNTA 150 mg every 6 hours, placebo and a single oral dose of moxifloxacin. Similarly, NUCYNTA had no relevant effect on other ECG parameters (heart rate, PR interval, QRS duration, T-wave or U-wave morphology).

Tapentadol produces peripheral vasodilation which may result in orthostatic hypotension or syncope. Manifestations of histamine release and/or peripheral vasodilation may include pruritus, flushing, red eyes, sweating, and/or orthostatic hypotension.

Effects on the Endocrine System

Opioids inhibit the secretion of adrenocorticotropic hormone (ACTH), cortisol, and luteinizing hormone (LH) in humans [see Adverse Reactions (6.2)]. They also stimulate prolactin, growth hormone (GH) secretion, and pancreatic secretion of insulin and glucagon.

Use of opioids for an extended period of time may influence the hypothalamic-pituitary-gonadal axis, leading to androgen deficiency that may manifest as low libido, impotence, erectile dysfunction, amenorrhea, or infertility. The causal role of opioids in the clinical syndrome of hypogonadism is unknown because the various medical, physical, lifestyle, and psychological stressors that may influence gonadal hormone levels have not been adequately controlled for in studies conducted to date [see Adverse Reactions (6.2)].

Effects on the Immune System

Opioids have been shown to have a variety of effects on components of the immune system in in vitro and animal models. The clinical significance of these findings is unknown. Overall, the effects of opioids appear to be modestly immunosuppressive.

Concentration-Efficacy Relationships

The minimum effective analgesic concentration will vary widely among patients, especially among patients who have been previously treated with opioid agonists. The minimum effective analgesic concentration of tapentadol for any individual patient may increase over time due to an increase in pain, the development of a new pain syndrome, and/or the development of analgesic tolerance [see Dosage and Administration (2.1, 2.6)].

Concentration-Adverse Experience Relationships

There is a relationship between increasing tapentadol plasma concentration and increasing frequency of dose-related adverse reactions such as nausea, vomiting, CNS effects, and respiratory depression. In opioid-tolerant patients, the situation may be altered by the development of tolerance to opioid-related adverse reactions [see Dosage and Administration (2.1, 2.6)].

12.3 PHARMACOKINETICS

Absorption

The mean absolute bioavailability after single-dose administration (fasting) of NUCYNTA is approximately 32% due to extensive first-pass metabolism. Maximum serum concentrations of tapentadol are typically observed at around 1.25 hours after dosing.

Dose-proportional increases in the Cmax and AUC values of tapentadol have been observed over the 50 to 150 mg dose range.

A multiple (every 6 hour) dose study with doses ranging from 75 to 175 mg tapentadol showed a mean accumulation factor of 1.6 for the parent drug and 1.8 for the major metabolite tapentadol-O-glucuronide, which are primarily determined by the dosing interval and apparent half-life of tapentadol and its metabolite.

Food Effect

The AUC and Cmax increased by 25% and 16%, respectively, when NUCYNTA was administered after a high-fat, high-calorie breakfast. NUCYNTA may be given with or without food.

Distribution

Tapentadol is widely distributed throughout the body. Following intravenous administration, the volume of distribution (Vz) for tapentadol is 540 +/- 98 L. The plasma protein binding is low and amounts to approximately 20%.

Elimination

Metabolism

In humans, about 97% of the parent compound is metabolized. Tapentadol is mainly metabolized via Phase 2 pathways, and only a small amount is metabolized by Phase 1 oxidative pathways.

The major pathway of tapentadol metabolism is conjugation with glucuronic acid to produce glucuronides. After oral administration approximately 70% (55% O-glucuronide and 15% sulfate of tapentadol) of the dose is excreted in urine in the conjugated form. A total of 3% of drug was excreted in urine as unchanged drug. Tapentadol is additionally metabolized to N-desmethyl tapentadol (13%) by CYP2C9 and CYP2C19 and to hydroxy tapentadol (2%) by CYP2D6, which are further metabolized by conjugation. Therefore, drug metabolism mediated by cytochrome P450 system is of less importance than phase 2 conjugation.

None of the metabolites contribute to the analgesic activity.

Excretion

Tapentadol and its metabolites are excreted almost exclusively (99%) via the kidneys. The terminal half-life is on average 4 hours after oral administration. The total clearance is 1530 +/-177 mL/min.

Specific Populations

Age: Geriatric Population

The mean exposure (AUC) to tapentadol was similar in elderly subjects compared to young adults, with a 16% lower mean Cmax observed in the elderly subject group compared to young adult subjects.

Hepatic Impairment

Administration of NUCYNTA resulted in higher exposures and serum levels to tapentadol in subjects with impaired hepatic function compared to subjects with normal hepatic function. The ratio of tapentadol pharmacokinetic parameters for the mild hepatic impairment group (Child-Pugh Score 5 to 6) and moderate hepatic impairment group (Child-Pugh Score 7 to 9) in comparison to the normal hepatic function group were 1.7 and 4.2, respectively, for AUC; 1.4 and 2.5, respectively, for Cmax; and 1.2 and 1.4, respectively, for t1/2. The rate of formation of tapentadol-O-glucuronide was lower in subjects with increased liver impairment.

Renal Impairment

AUC and Cmax of tapentadol were comparable in subjects with varying degrees of renal function (from normal to severely impaired). In contrast, increasing exposure (AUC) to tapentadol-O-glucuronide was observed with increasing degree of renal impairment. In subjects with mild (CLCR = 50 to <80 mL/min), moderate (CLCR = 30 to <50 mL/min), and severe (CLCR

= <30 mL/min) renal impairment, the AUC of tapentadol-O-glucuronide was 1.5-, 2.5-, and 5.5- fold higher compared with normal renal function, respectively.

Drug Interaction Studies

Pharmacokinetic Drug Interactions

Tapentadol is mainly metabolized by Phase 2 glucuronidation, a high capacity/low affinity system; therefore, clinically relevant interactions caused by Phase 2 metabolism are unlikely to occur. Naproxen and probenecid increased the AUC of tapentadol by 17% and 57%, respectively. These changes are not considered clinically relevant and no change in dose is required.

No changes in the pharmacokinetic parameters of tapentadol were observed when acetaminophen and acetylsalicylic acid were given concomitantly.

In vitro studies did not reveal any potential of tapentadol to either inhibit or induce cytochrome P450 enzymes. Furthermore, a minor amount of NUCYNTA is metabolized via the oxidative pathway. Thus, clinically relevant interactions mediated by the cytochrome P450 system are unlikely to occur.

The pharmacokinetics of tapentadol were not affected when gastric pH or gastrointestinal motility were increased by omeprazole and metoclopramide, respectively.

Plasma protein binding of tapentadol is low (approximately 20%). Therefore, the likelihood of pharmacokinetic drug-drug interactions by displacement from the protein binding site is low.

Age: Pediatric Population

In the pediatric population the maximum serum concentrations were observed at a similar time to adults, with no age-related changes.

A summary of the simulated steady-state exposure levels across dosing interval tau (AUCtau,ss) among the two pediatric age groups receiving 1.25 mg/kg oral solution q4h compared with adult doses is in Table 3.

Table 3. Simulated median steady-state tapentadol area under the curve across dosing interval tau (AUCtau,ss) in pediatric and adult subjects receiving tapentadol every 4 hours (q4h) for 5 days
Simulated AUCtau,ss | Pediatric Dose (1.25 mg/kg) |  | Adult Doses
Group | 6 to <12y | 12 to <18y | 50 mg | 75 mg | 100 mg
AUC (ng∙h/mL)
Median | 309 | 369 | 217 | 325 | 434
2.5th – 97.5th PCT | (197 – 487) | (233 – 563) | (131 – 353) | (196 – 529) | (262 – 706)]

13 NON-CLINICAL TOXICOLOGY

13.1 CARCINOGENESIS, MUTAGENESIS, IMPAIRMENT OF FERTILITY

Carcinogenesis

Tapentadol was administered to rats (diet) and mice (oral gavage) for two years.

In mice, tapentadol HCl was administered by oral gavage at dosages of 50, 100 and 200 mg/kg/day for 2 years (up to 0.2 times the plasma exposure at the maximum recommended human dose [MRHD] on an area under the time-curve [AUC] basis). No increase in tumor incidence was observed at any dose level.

In rats, tapentadol HCl was administered in diet at dosages of 10, 50, 125 and 250 mg/kg/day for two years (up to 0.2 times in the male rats and 0.6 times in the female rats the MRHD on an AUC basis). No increase in tumor incidence was observed at any dose level.

Mutagenesis

Tapentadol did not induce gene mutations in bacteria, but was clastogenic with metabolic activation in a chromosomal aberration test in V79 cells. The test was repeated and was negative in the presence and absence of metabolic activation. The one positive result for tapentadol was not confirmed in vivo in rats, using the two endpoints of chromosomal aberration and unscheduled DNA synthesis, when tested up to the maximum tolerated dose.

Impairment of Fertility

Tapentadol HCl was administered intravenously to male or female rats at dosages of 3, 6, or 12 mg/kg/day (representing exposures of up to approximately 0.4 times the exposure at the MRHD on an AUC basis, based on extrapolation from toxicokinetic analyses in a separate

4-week intravenous study in rats). Tapentadol did not alter fertility at any dose level. Maternal toxicity and adverse effects on embryonic development, including decreased number of implantations, decreased numbers of live conceptuses, and increased pre- and post-implantation losses occurred at dosages ≥6 mg/kg/day.

13.2 ANIMAL TOXICOLOGY AND/OR PHARMACOLOGY

In toxicological studies with tapentadol, the most common systemic effects of tapentadol were related to the mu-opioid receptor agonist and norepinephrine reuptake inhibition pharmacodynamic properties of the compound. Transient, dose-dependent and predominantly CNS-related findings were observed, including impaired respiratory function and convulsions, the latter occurring in the dog at plasma levels (Cmax) which are in the range associated with the maximum recommended human dose (MRHD).

14 CLINICAL STUDIES

14.1 CLINICAL STUDIES IN ADULT PATIENTS

The efficacy and safety of NUCYNTA tablets in the treatment of acute pain has been established in two randomized, double-blind, placebo- and active-controlled studies of moderate to severe pain from first metatarsal bunionectomy and end-stage degenerative joint disease.

Orthopedic Surgery – Bunionectomy

A randomized, double-blind, parallel-group, active- and placebo-controlled, multiple-dose study demonstrated the efficacy of 50 mg, 75 mg, and 100 mg NUCYNTA tablets given every 4 to 6 hours for 72 hours in patients aged 18 to 80 years experiencing moderate to severe pain following unilateral, first metatarsal bunionectomy surgery. Patients who qualified for the study with a baseline pain score of ≥4 on an 11-point rating scale ranging from 0 to 10 were randomized to 1 of 5 treatments. Patients were allowed to take a second dose of study medication as soon as 1 hour after the first dose on study Day 1, with subsequent dosing every 4 to 6 hours. If rescue analgesics were required, the patients were discontinued for lack of efficacy. Efficacy was evaluated by comparing the sum of pain intensity difference over the first 48 hours (SPID48) versus placebo. NUCYNTA tablets at each dose provided a greater reduction in pain compared to placebo based on SPID48 values.

For various degrees of improvement from baseline to the 48-hour endpoint, Figure 1 shows the fraction of patients achieving that level of improvement. The figures are cumulative, such that every patient that achieves a 50% reduction in pain from baseline is included in every level of improvement below 50%. Patients who did not complete the 48-hour observation period in the study were assigned 0% improvement.

Figure 1. Percentage of Patients Achieving Various Levels of Pain Relief as Measured by Pain Severity at 48 Hours Compared to Baseline- Post Operative Bunionectomy

The proportions of patients who showed reduction in pain intensity at 48 hours of 30% or greater, or 50% or greater were significantly higher in patients treated with NUCYNTA tablets at each dose versus placebo.

End-Stage Degenerative Joint Disease

A randomized, double-blind, parallel-group, active- and placebo-controlled, multiple-dose study evaluated the efficacy and safety of 50 mg and 75 mg NUCYNTA tablets given every 4 to 6 hours during waking hours for 10 days in patients aged 18 to 80 years, experiencing moderate to severe pain from end stage degenerative joint disease of the hip or knee, defined as a 3-day mean pain score of ≥5 on an 11-point pain intensity scale, ranging from 0 to 10. Pain scores were assessed twice daily and assessed the pain the patient had experienced over the previous 12 hours. Patients were allowed to continue non-opioid analgesic therapy for which they had been on a stable regimen before screening throughout the study. Eighty-three percent (83%) of patients in the tapentadol treatment groups and the placebo group took such analgesia during the study. The 75 mg treatment group was dosed at 50 mg for the first day of the study, followed by 75 mg for the remaining nine days. Patients requiring rescue analgesics other than study medication were discontinued for lack of efficacy. Efficacy was evaluated by comparing the sum of pain intensity difference (SPID) versus placebo over the first five days of treatment. NUCYNTA tablets 50 mg and 75 mg provided improvement in pain compared with placebo based on the 5-Day SPID.

For various degrees of improvement from baseline to the Day 5 endpoint, Figure 2 shows the fraction of patients achieving that level of improvement. The figures are cumulative, such that every patient that achieves a 50% reduction in pain from baseline is included in every level of improvement below 50%. Patients who did not complete the 5-day observation period in the study were assigned 0% improvement.

Figure 2. Percentage of Patients Achieving Various Levels of Pain Relief as Measured by Average Pain Severity for the Previous 12 hours, Measured on Study Day 5 Compared to Baseline -- End Stage Degenerative Joint Disease

The proportions of patients who showed reduction in pain intensity at 5 days of 30% or greater, or 50% or greater were significantly higher in patients treated with NUCYNTA tablets at each dose versus placebo.

14.2 CLINICAL STUDY IN PEDIATRIC PATIENTS

The efficacy and safety of NUCYNTA (tapentadol) tablets for the management of acute pain severe enough to require an opioid analgesic and for which alternative treatments are inadequate in pediatric patients who are 6 years and older and weigh at least 40 kg have been established based on one randomized, double-blind, placebo-controlled, multiple-dose study of NUCYNTA (tapentadol) oral solution in pediatric patients ages birth to 17 years who had undergone surgery that would reliably produce moderate to severe acute post-operative pain.

Patients who had undergone surgery that would reliably produce moderate to severe acute pain requiring opioid treatment via nurse-controlled analgesia (NCA) or patient-controlled analgesia (PCA), had received postoperative morphine or hydromorphone by NCA or PCA, and were able to tolerate liquids were randomized to either NUCYNTA (tapentadol) oral solution or placebo (2:1 allocation). Patients from 6 months to 17 years of age were administered NUCYNTA (tapentadol) oral solution 1.25 mg/kg body weight (maximum single dose 100 mg) or the same volume of placebo every four hours for the first 24 hours with dose reduction to 1.0 mg/kg body weight after 24 hours if there was a reduced need for analgesia at the investigator's discretion.

The study was statistically powered to evaluate the efficacy of NUCYNTA (tapentadol) oral solution across the pediatric age range from 2 to 17 years of age. Efficacy was evaluated by comparing the total amount of supplemental opioid analgesic medication (morphine equivalents in mg/kg body weight) used within 12 hours and 24 hours following initiation of study drug between the NUCYNTA (tapentadol) oral solution and placebo groups. Overall, statistically significantly more supplemental opioid analgesic medication was used in the placebo group than in the NUCYNTA (tapentadol) oral solution group during the first 12 and 24 hours after first dose of study drug. However, a descriptive analysis of supplemental opioid analgesic medication used by age subgroup demonstrated lack of efficacy of NUCYNTA (tapentadol) oral solution in pediatric patients 2 to less than 6 years of age [see Pediatric Use (8.4)].

The descriptive analysis of supplemental opioid analgesic medication use showed the following results (see Table 4):

- Numerically more supplemental opioid analgesic medication used in the placebo group than in the NUCYNTA (tapentadol) oral solution group at 12 hours and 24 hours for both the 6 to less than 12 years age group and the 12 to less than 18 years age group indicating that NUCYNTA (tapentadol) oral solution is effective in pediatric patients 6 years of age and older.
- No numerical difference in supplemental opioid analgesic medication used between the NUCYNTA (tapentadol) oral solution and placebo groups at 12 hours and numerically more supplemental opioid analgesic medication used in the NUCYNTA (tapentadol) oral solution group than in the placebo group at 24 hours for the 2 to less than 6 years age group indicating that NUCYNTA (tapentadol) oral solution is not effective in pediatric patients less than 6 years of age.

NUCYNTA (tapentadol) tablets are not approved for use in pediatric patients less than 6 years of age or who weigh less than 40 kg [see Pediatric Use (8.4)].

The efficacy and safety of NUCYNTA (tapentadol) tablets at doses higher than 1.25 mg/kg body weight (maximum single dose of 100 mg) have not been studied; therefore, the use of NUCYNTA (tapentadol) tablets at doses higher than 1.25 mg/kg body weight is not recommended [see Dosage and Administration (2.4)].

Table 4. Descriptive Analysis of the Amount of Supplemental Opioid Analgesic Medication Used Within the First 12 and 24 Hours by Age Subgroup in Pediatric Patients from 2 to Less Than 18 Years of Age
 | Placebo |  | NUCYNTA (tapentadol) oral solution |  | Difference (95% CI)
 | n | LS Mean | n | LS Mean | Difference (95% CI)
12 hours
Overall (2 to <18 years) | 52 | 0.129 | 108 | 0.082 | -0.047 (-0.091, -0.002) [p-value = 0.0404;]
12 to <18 years | 25 | 0.212 | 53 | 0.142 | -0.070 (-0.155, 0.014)
6 to < 12 years | 15 | 0.111 | 32 | 0.064 | -0.047 (-0.105, 0.012)
2 to < 6 years | 12 | 0.044 | 23 | 0.046 | 0.002 (-0.038, 0.042)
24 hours
Overall (2 to <18 years) | 52 | 0.237 | 108 | 0.139 | -0.097 (-0.176, -0.019) [p-value = 0.0154]
12 to <18 years | 25 | 0.406 | 53 | 0.239 | -0.167 (-0.311, -0.022)
6 to < 12 years | 15 | 0.196 | 32 | 0.122 | -0.074 (-0.185, 0.037)
2 to < 6 years | 12 | 0.066 | 23 | 0.082 | 0.016 (-0.049, 0.080)

16 HOW SUPPLIED/STORAGE AND HANDLING

NUCYNTA Tablets are available in the following strengths and packages. All tablets are round and biconvex-shaped.

50 mg tablets are yellow and debossed with "O-M" on one side and "50" on the other side, and are available in bottles of 100 (NDC 24510-050-10) and hospital unit dose blister packs of 10 (NDC 24510-050-01).

75 mg tablets are yellow-orange and debossed with "O-M" on one side and "75" on the other side, and are available in bottles of 100 (NDC 24510-075-10) and hospital unit dose blister packs of 10 (NDC 24510-075-01).

100 mg tablets are orange and debossed with "O-M" on one side and "100" on the other side, and are available in bottles of 100 (NDC 24510-100-10) and hospital unit dose blister packs of 10 (NDC 24510-100-01).

Storage and Handling

Store at 20°C-25°C (68°F-77°F); excursions permitted to 15° - 30°C (59° - 86°F) [see USP Controlled Room Temperature]. Protect from moisture.

Keep NUCYNTA tablets in a secure place out of reach of children.

NUCYNTA tablets that are no longer needed should be destroyed by flushing down the toilet.

Store NUCYNTA Tablets securely and dispose of properly [see Patient Counseling Information (17)].

17 PATIENT COUNSELING INFORMATION

Advise the patient to read the FDA-approved patient labeling (Medication Guide).

Storage and Disposal

Because of the risks associated with accidental ingestion, misuse, and abuse, advise patients to store NUCYNTA tablets securely, out of sight and reach of children, and in a location not accessible by others, including visitors to the home. Inform patients that leaving NUCYNTA Tablets unsecured can pose a deadly risk to others in the home [see Warnings and Precautions (5.1, 5.2), Drug Abuse and Dependence (9.2)].

Advise patients and caregivers that when medicines are no longer needed, they should be disposed of promptly. Expired, unwanted, or unused NUCYNTA Tablets should be disposed of by flushing the unused medication down the toilet if a drug take-back option is not readily available. Inform patients that they can visit www.fda.gov/drugdisposal for a complete list of medicines recommended for disposal by flushing, as well as additional information on disposal of unused medicines.

Addiction, Abuse, and Misuse

Inform patients that the use of NUCYNTA tablets, even when taken as recommended, can result in addiction, abuse, and misuse, which can lead to overdose and death [see Warnings and Precautions (5.1)]. Instruct patients not to share NUCYNTA tablets with others and to take steps to protect NUCYNTA tablets from theft or misuse.

Life-Threatening Respiratory Depression

Inform patients of the risk of life-threatening respiratory depression, including information that the risk is greatest when starting NUCYNTA tablets or when the dosage is increased, and that it can occur even at recommended dosages.

Educate patients and caregivers on how to recognize respiratory depression and emphasize the importance of calling 911 or getting emergency medical help right away in the event of a known or suspected overdose [see Warnings and Precautions (5.2)].

Accidental Ingestion

Inform patients that accidental ingestion, especially by children, may result in respiratory depression or death [see Warnings and Precautions (5.2)].

Interactions with Benzodiazepines and other CNS Depressants

Inform patients and caregivers that potentially fatal additive effects may occur if NUCYNTA tablets are used with benzodiazepines or other CNS depressants including alcohol (e.g., non-benzodiazepine sedative/hypnotics, anxiolytics, tranquilizers, muscle relaxants, general anesthetics, antipsychotics, gabapentinoids [gabapentin or pregabalin], and other opioids), and not to use these concomitantly unless supervised by a health care provider [see Warnings and Precautions (5.3), Drug Interactions (7)].

Patient Access to an Opioid Overdose Reversal Agent for the Emergency Treatment of Opioid Overdose

Inform patients and caregivers about opioid overdose reversal agents (e.g., naloxone, nalmefene). Discuss the importance of having access to an opioid overdose reversal agent, especially if the patient has risk factors for overdose (e.g., concomitant use of CNS depressants, a history of opioid use disorder, or prior opioid overdose) or if there are household members (including children) or other close contacts at risk for accidental ingestion or opioid overdose.

Discuss with the patient the options for obtaining an opioid overdose reversal agent (e.g., prescription, over-the-counter, or as part of a community-based program) [see Dosage and Administration (2.2), Warnings and Precautions (5.2)].

Educate patients and caregivers on how to recognize the signs and symptoms of an overdose.

Explain to patients and caregivers that effects of opioid overdose reversal agents like naloxone and nalmefene are temporary, and that they must call 911 or get emergency medical help right away in all cases of known or suspected opioid overdose, even if an opioid overdose reversal agent is administered [see Overdosage (10)].

Advise patients and caregivers:

- how to treat with the overdose reversal agent in the event of an opioid overdose
- to tell family and friends about their opioid overdose reversal agent, and to keep it in a place where family and friends can access it in an emergency
- to read the Patient Information (or other educational material) that will come with their opioid overdose reversal agent. Emphasize the importance of doing this before an opioid emergency happens, so the patient and caregiver will know what to do.

Hyperalgesia and Allodynia

Inform patients and caregivers not to increase opioid dosage without first consulting a clinician. Advise patients to seek medical attention if they experience symptoms of hyperalgesia, including worsening pain, increased sensitivity to pain, or new pain [see Warnings and Precautions (5.5), Adverse Reactions (6.2)].

Serotonin Syndrome

Inform patients that opioids could cause a rare but potentially life-threatening condition called serotonin syndrome resulting from concomitant administration of serotonergic drugs. Warn patients of the symptoms of serotonin syndrome and to seek medical attention right away if symptoms develop. Instruct patients to inform their healthcare providers if they are taking, or plan to take serotonergic medications [see Warnings and Precautions (5.7), Drug Interactions (7)].

MAOI Interaction

Inform patients not to take NUCYNTA tablets while using any drugs that inhibit monoamine oxidase. Patients should not start MAOIs while taking NUCYNTA tablets [see Warnings and Precautions (5.7), Drug Interactions (7)].

Important Administration Instructions

Instruct patients how to properly take NUCYNTA tablets, including the following:

- Advise patients not to adjust the dose of NUCYNTA tablets without consulting with a physician or other healthcare professional.

Important Discontinuation Instructions

- In order to avoid developing withdrawal symptoms, instruct patients not to discontinue NUCYNTA tablets without first discussing a tapering plan with the prescriber [see Dosage and Administration (2.7)]

Driving or Operating Heavy Machinery

Inform patients that NUCYNTA tablets may impair the ability to perform potentially hazardous activities such as driving a car or operating heavy machinery. Advise patients not to perform such tasks until they know how they will react to the medication [see Warnings and Precautions (5.15)].

Constipation

Advise patients of the potential for severe constipation, including management instructions and when to seek medical attention [see Adverse Reactions (6.1)].

Adrenal Insufficiency

Inform patients that opioids could cause adrenal insufficiency, a potentially life-threatening condition. Adrenal insufficiency may present with non-specific symptoms and signs such as nausea, vomiting, anorexia, fatigue, weakness, dizziness, and low blood pressure. Advise patients to seek medical attention if they experience a constellation of these symptoms [see Warnings and Precautions (5.9)].

Hypotension

Inform patients that NUCYNTA tablets may cause orthostatic hypotension and syncope. Instruct patients how to recognize symptoms of low blood pressure and how to reduce the risk of serious consequences should hypotension occur (e.g., sit or lie down, carefully rise from a sitting or lying position) [see Warnings and Precautions (5.10)].

Anaphylaxis

Inform patients that anaphylaxis has been reported with ingredients contained in NUCYNTA tablets. Advise patients how to recognize such a reaction and when to seek medical attention [see Contraindications (4), Adverse Reactions (6.2)].

Pregnancy

Neonatal Opioid Withdrawal Syndrome

Inform female patients of reproductive potential that use of NUCYNTA tablets for an extended period of time during pregnancy can result in neonatal opioid withdrawal syndrome, which may be life-threatening if not recognized and treated [see Warnings and Precautions (5.4), Use in Specific Populations (8.1)].

Embryo-Fetal Toxicity

Inform female patients of reproductive potential that NUCYNTA tablets can cause fetal harm and to inform the healthcare provider of a known or suspected pregnancy [see Use in Specific Populations (8.1)].

Lactation

Advise nursing mothers to carefully observe infants for increased sleepiness (more than usual), breathing difficulties, or limpness. Instruct nursing mothers to seek immediate medical care if they notice these signs [see Use in Specific Populations (8.2)].

Infertility

Inform patients that use of opioids for an extended period of time may cause reduced fertility. It is not known whether these effects on fertility are reversible [see Use in Specific Populations (8.3)]

Distributed by: Collegium Pharmaceutical, Inc., Stoughton, MA 02072

NUC-021-C.11

Medication Guide
NUCYNTA (new-SINN-tah)
(tapentadol) tablets , CII

NUCYNTA tablets are:

- A strong prescription pain medicine that contains an opioid (narcotic) that is used to manage short term (acute) pain in adults and children 6 years of age and older who weigh at least 88 pounds (40 kg), when other pain treatments such as non-opioid pain medicines do not treat your pain well enough or you cannot tolerate them.
- An opioid pain medicine that can put you at risk for overdose and death. Even if you take your dose correctly as prescribed you are at risk for opioid addiction, abuse, and misuse that can lead to death.

Important information about NUCYNTA tablets:

- Get emergency help or call 911 right away if you take too much NUCYNTA (overdose) tablets. When you first start taking NUCYNTA tablets, when your dose is changed, or if you take too much (overdose), serious or life- threatening breathing problems that can lead to death may occur. Ask your healthcare provider about medicines like naloxone or nalmefene that can be used in an emergency to reverse an opioid overdose.
- Taking NUCYNTA tablets with other opioid medicines, benzodiazepines, gabapentinoids (gabapentin or pregabalin), alcohol, or other central nervous system depressants (including street drugs) can cause severe drowsiness, decreased awareness, breathing problems, coma, and death.
- Never give anyone else your NUCYNTA tablets. They could die from taking it. Selling or giving away NUCYNTA tablets is against the law.
- Store NUCYNTA tablets securely, out of sight and reach of children, and in a location not accessible by others, including visitors to the home.

Do not take NUCYNTA tablets if you have:

- severe asthma, trouble breathing, or other lung problems.
- a bowel blockage or have narrowing of the stomach or intestines.

Before taking NUCYNTA tablets, tell your healthcare provider if you have a history of:

- head injury, seizures
- problems urinating

- liver, kidney, thyroid problems
- pancreas or gallbladder problems

- abuse of street or prescription drugs, alcohol addiction, opioid overdose or mental health problems.

Tell your healthcare provider if you are:

- noticing your pain getting worse. If your pain gets worse after you take NUCYNTA tablets, do not take more NUCYNTA tablets without first talking to your healthcare provider. Tell your healthcare provider if the pain that you have increases, if you feel more sensitive to pain, or if you have new pain after taking NUCYNTA tablets.
- pregnant or planning to become pregnant. Prolonged use of NUCYNTA tablets during pregnancy can cause withdrawal symptoms in your newborn baby that could be life-threatening if not recognized and treated.
- breastfeeding. NUCYNTA tablets pass into breast milk and may harm your baby. Carefully observe infants for increased sleepiness (more than usual), breathing difficulties, or limpness. Seek immediate medical care if you notice these signs.
- living in a household where there are small children or someone who has abused street or prescription drugs.
- taking prescription or over-the-counter medicines, vitamins, or herbal supplements. Taking NUCYNTA tablets with certain other medicines can cause serious side effects that could lead to death.

When taking NUCYNTA tablets:

- Do not change your dose. Take NUCYNTA tablets exactly as prescribed by your healthcare provider. Use the lowest dose possible for the shortest time needed.
- For acute (short-term) pain, you may only need to take NUCYNTA tablets for a few days. You may have some NUCYNTA tablets left over that you did not use. See disposal information at the bottom of this section for directions on how to safely throw away (dispose of) your unused NUCYNTA tablets.
- Take your prescribed dose every 4-6 hours as needed for pain, at the same time every day. Do not take more than your prescribed dose. If you miss a dose, take your next dose at your usual time.
- Call your healthcare provider if the dose you are taking does not control your pain.

- If you have been taking NUCYNTA tablets regularly, do not stop taking NUCYNTA tablets without talking to your healthcare provider.
- Dispose of expired, unwanted, or unused NUCYNTA Tablets by promptly flushing down the toilet, if a drug take-back option is not readily available. Visit www.fda.gov/drugdisposal for additional information on disposal of unused medicines.

While taking NUCYNTA tablets DO NOT:

- Drive or operate heavy machinery, until you know how NUCYNTA tablets affect you. NUCYNTA tablets can make you sleepy, dizzy, or lightheaded.
- Drink alcohol or use prescription or over-the-counter medicines that contain alcohol. Using products containing alcohol during treatment with NUCYNTA tablets may cause you to overdose and die.

The possible side effects of NUCYNTA tablets:

- constipation, nausea, sleepiness, vomiting, tiredness, headache, dizziness, abdominal pain. Call your healthcare provider if you have any of these symptoms and they are severe.

Get emergency medical help or call 911 right away if you have:

- trouble breathing, shortness of breath, fast heartbeat, chest pain, swelling of your face, tongue, or throat, extreme drowsiness, light-headedness when changing positions, feeling faint, agitation, high body temperature, trouble walking, stiff muscles, or mental changes such as confusion.

These are not all the possible side effects of NUCYNTA tablets. Call your healthcare provider for medical advice about side effects. You may report side effects to FDA at 1-800-FDA-1088. For more information go to dailymed.nlm.nih.gov
Distributed by: Collegium Pharmaceutical, Inc., 100 Technology Center Drive Suite 300, Stoughton, MA, 02072, www.collegiumpharma.com or call 1-855-331-5615.

This Medication Guide has been approved by the U.S. Food and Drug Administration

NUC-022-C.6 Issued: 12/2025

PRINCIPAL DISPLAY PANEL - 50 mg Tablet Bottle Label

NDC 24510-050-10
100 Tablets

NUCYNTA®
(tapentadol) Tablets

50 mg

CII

Each tablet contains:
tapentadol 50 mg

Caution: Federal law prohibits the transfer
of this drug to any person other than the patient
for whom it was prescribed.

Dispense the accompanying Medication Guide
to each patient.

Rev Dec 2018
NUC-003-C.4

PRINCIPAL DISPLAY PANEL - 75 mg Tablet Bottle Label

NDC 24510-075-10
100 Tablets

NUCYNTA®
(tapentadol) Tablets

75 mg

CII

Each tablet contains:
tapentadol 75 mg

Caution: Federal law prohibits the transfer
of this drug to any person other than the patient
for whom it was prescribed.

Dispense the accompanying Medication Guide
to each patient.

Rev Dec 2018
NUC-006-C.4

PRINCIPAL DISPLAY PANEL - 100 mg Tablet Bottle Label

NDC 24510-100-10
100 Tablets

NUCYNTA®
(tapentadol) Tablets

100 mg

CII

Each tablet contains:
tapentadol 100 mg

Caution: Federal law prohibits the transfer
of this drug to any person other than the patient
for whom it was prescribed.

Dispense the accompanying Medication Guide
to each patient.

Rev Dec 2018
NUC-009-C.4